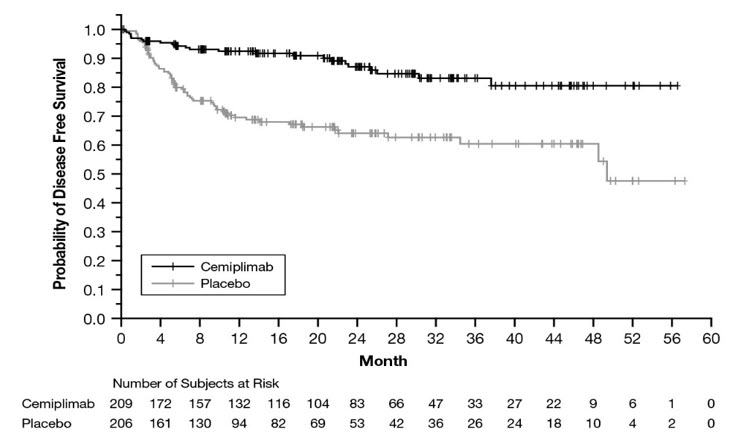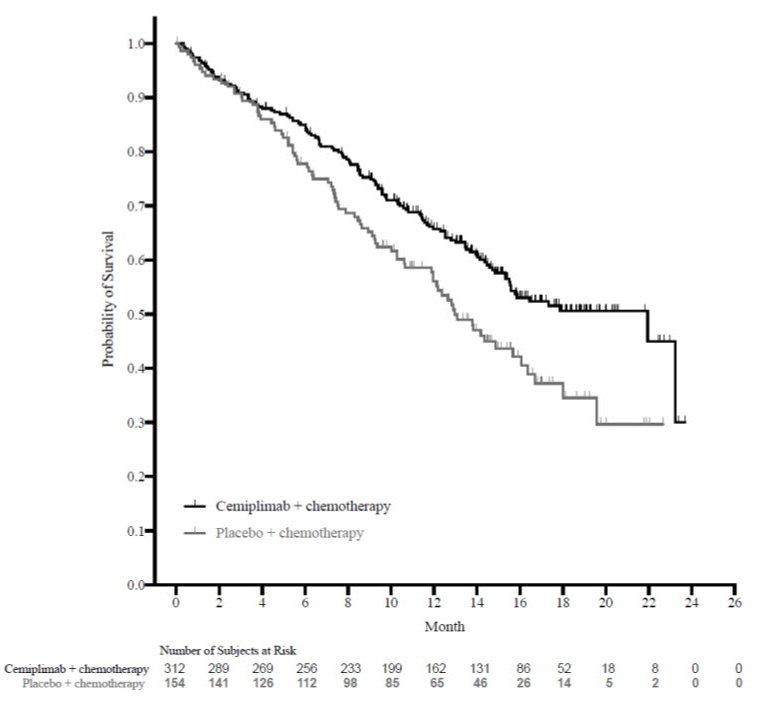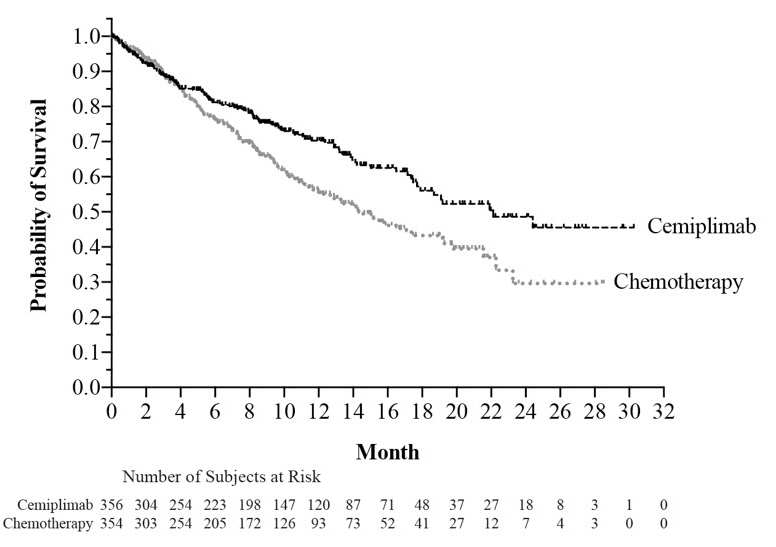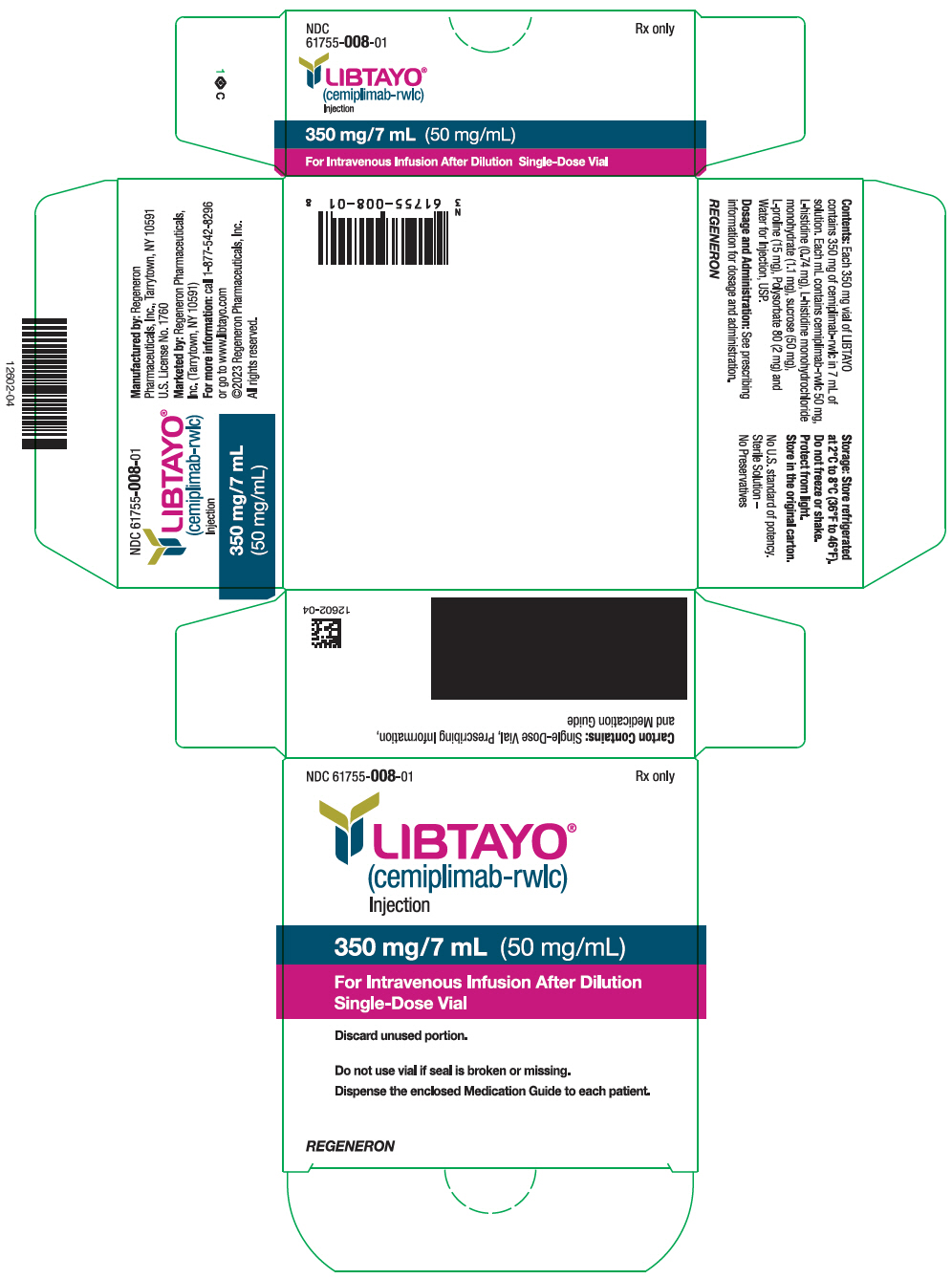 DRUG LABEL: LIBTAYO
NDC: 61755-008 | Form: INJECTION
Manufacturer: Regeneron Pharmaceuticals, Inc.
Category: prescription | Type: HUMAN PRESCRIPTION DRUG LABEL
Date: 20251029

ACTIVE INGREDIENTS: CEMIPLIMAB 50 mg/1 mL
INACTIVE INGREDIENTS: HISTIDINE 0.74 mg/1 mL; HISTIDINE MONOHYDROCHLORIDE MONOHYDRATE 1.1 mg/1 mL; PROLINE 15 mg/1 mL; POLYSORBATE 80 2 mg/1 mL; SUCROSE 50 mg/1 mL; WATER

HIGHLIGHTS OF PRESCRIBING INFORMATION

These highlights do not include all the information needed to use LIBTAYO safely and effectively. See full prescribing information for LIBTAYO.
LIBTAYO® (cemiplimab-rwlc) injection, for intravenous use
Initial U.S. Approval: 2018

RECENT MAJOR CHANGES

Indications and Usage (1.1) | 10/2025
Dosage and Administration (2.2) | 10/2025

1 INDICATIONS AND USAGE

LIBTAYO is a programmed death receptor-1 (PD-1) blocking antibody indicated:

Cutaneous Squamous Cell Carcinoma (CSCC)

- for the treatment of adult patients with metastatic cutaneous squamous cell carcinoma (mCSCC) or locally advanced CSCC (laCSCC) who are not candidates for curative surgery or curative radiation. (1.1)
- for the adjuvant treatment of adult patients with CSCC at high risk of recurrence after surgery and radiation. (1.1, 14.1)

Basal Cell Carcinoma (BCC)

- for the treatment of adult patients with locally advanced or metastatic BCC (laBCC or mBCC) who have been previously treated with a hedgehog pathway inhibitor or for whom a hedgehog pathway inhibitor is not appropriate. (1.2)

Non-Small Cell Lung Cancer (NSCLC)

- in combination with platinum‐based chemotherapy for the first‐line treatment of adult patients with non-small cell lung cancer (NSCLC) with no EGFR, ALK or ROS1 aberrations and is:
  - locally advanced where patients are not candidates for surgical resection or definitive chemoradiation or
  - metastatic. (1.3)
- as single agent for the first-line treatment of adult patients with NSCLC whose tumors have high PD-L1 expression [Tumor Proportion Score (TPS) ≥50%] as determined by an FDA-approved test, with no EGFR, ALK or ROS1 aberrations, and is:
  - locally advanced where patients are not candidates for surgical resection or definitive chemoradiation or
  - metastatic. (1.3, 2.1)

2 DOSAGE AND ADMINISTRATION

Administer LIBTAYO as an intravenous infusion over 30 minutes after dilution. (2.2)

- Metastatic and locally advanced CSCC and BCC: 350 mg every 3 weeks until disease progression, unacceptable toxicity, or up to 24 months. (2.2)
- Adjuvant treatment of CSCC at high risk of recurrence after surgery and radiation:
  - 350 mg every 3 weeks for 12 weeks followed by 700 mg every 6 weeks until disease recurrence, unacceptable toxicity, or up to 48 weeks of total therapy, or
  - 350 mg every 3 weeks until disease recurrence, unacceptable toxicity, or up to 48 weeks of total therapy. (2.2)
- NSCLC: 350 mg every 3 weeks until disease progression or unacceptable toxicity. (2.2)

3 DOSAGE FORMS AND STRENGTHS

Injection: 350 mg/7 mL (50 mg/mL) solution in a single-dose vial. (3)

4 CONTRAINDICATIONS

None. (4)

5 WARNINGS AND PRECAUTIONS

- Immune-Mediated Adverse Reactions (5.1)
  - Immune-mediated adverse reactions, which may be severe or fatal, can occur in any organ system or tissue, including the following: immune-mediated pneumonitis, immune-mediated colitis, immune-mediated hepatitis, immune-mediated endocrinopathies, immune-mediated dermatologic adverse reactions, immune-mediated nephritis and renal dysfunction, and solid organ transplant rejection.
  - Monitor for early identification and management. Evaluate liver enzymes, creatinine, and thyroid function at baseline and periodically during treatment.
  - Withhold or permanently discontinue LIBTAYO based on the severity of reaction. (2.3)
- Infusion-Related Reactions: Interrupt, slow the rate of infusion, or permanently discontinue based on severity of reaction. (2.3, 5.2)
- Complications of Allogeneic Hematopoietic Stem Cell Transplantation (HSCT): Fatal and other serious complications can occur in patients who receive allogeneic HSCT before or after being treated with a PD-1/PD-L1 blocking antibody. (5.3)
- Embryo-Fetal Toxicity: Can cause fetal harm. Advise females of reproductive potential of the potential risk to a fetus and use of effective contraception. (5.4, 8.1, 8.3)

6 ADVERSE REACTIONS

Most common adverse reactions (≥15%):

LIBTAYO as a single agent in mCSCC or laCSCC, mBCC or laBCC, and NSCLC with high PD-L1 expression:

- Fatigue, musculoskeletal pain, rash, diarrhea, and anemia. (6.1)

LIBTAYO as a single agent in adjuvant CSCC at high risk of recurrence:

- Rash and pruritus. (6.1)

LIBTAYO in combination with platinum-based chemotherapy in NSCLC:

- Alopecia, musculoskeletal pain, nausea, fatigue, peripheral neuropathy, and decreased appetite. (6.1)

To report SUSPECTED ADVERSE REACTIONS, contact Regeneron at 1-877-542-8296 or FDA at 1-800-FDA-1088 or www.fda.gov/medwatch.

8 USE IN SPECIFIC POPULATIONS

Lactation: Advise not to breastfeed. (8.2)

FULL PRESCRIBING INFORMATION

1 INDICATIONS AND USAGE

1.1 Cutaneous Squamous Cell Carcinoma

LIBTAYO is indicated for the treatment of adult patients with metastatic cutaneous squamous cell carcinoma (mCSCC) or locally advanced CSCC (laCSCC) who are not candidates for curative surgery or curative radiation.

LIBTAYO is indicated for the adjuvant treatment of adult patients with CSCC at high risk of recurrence [see Clinical Studies (14.1)] after surgery and radiation.

1.2 Basal Cell Carcinoma

LIBTAYO is indicated for the treatment of adult patients with locally advanced or metastatic basal cell carcinoma (laBCC or mBCC) who have been previously treated with a hedgehog pathway inhibitor or for whom a hedgehog pathway inhibitor is not appropriate.

1.3 Non-Small Cell Lung Cancer

LIBTAYO in combination with platinum‐based chemotherapy is indicated for the first‐line treatment of adult patients with non-small cell lung cancer (NSCLC) with no EGFR, ALK or ROS1 aberrations and is:

- locally advanced where patients are not candidates for surgical resection or definitive chemoradiation or
- metastatic.

LIBTAYO as a single agent is indicated for the first-line treatment of adult patients with NSCLC whose tumors have high PD-L1 expression [Tumor Proportion Score (TPS) ≥50%] as determined by an FDA-approved test [see Dosage and Administration (2.1)], with no EGFR, ALK or ROS1 aberrations, and is:

- locally advanced where patients are not candidates for surgical resection or definitive chemoradiation or
- metastatic.

2 DOSAGE AND ADMINISTRATION

2.1 Patient Selection for NSCLC

Select patients with locally advanced or metastatic NSCLC for treatment with LIBTAYO as a single agent based on PD-L1 expression on tumor cells [see Clinical Studies (14.3)].

Information on FDA-approved tests for the detection of PD-L1 expression is available at: http://www.fda.gov/CompanionDiagnostics.

2.2 Recommended Dosage

The recommended dosages of LIBTAYO are presented in Table 1.

Refer to the Prescribing Information for the agents administered in combination with LIBTAYO for recommended dosing information, as appropriate.

Table 1: Recommended Dosages of LIBTAYO as a Single Agent or in Combination with Other Agents
Indication | Recommended dosage of LIBTAYO as an intravenous infusion | Duration of Treatment
Adults with metastatic cutaneous squamous cell carcinoma (mCSCC) or locally advanced CSCC (laCSCC) | 350 mg every 3 weeks | Until disease progression, unacceptable toxicity, or up to 24 months.
Adjuvant treatment of adult patients with CSCC at high risk of recurrence after surgery and radiation | 350 mg every 3 weeks for 12 weeks, followed by 700 mg every 6 weeks Or 350 mg every 3 weeks | Until disease recurrence, unacceptable toxicity, or up to 48 weeks.
Adults with locally advanced basal cell carcinoma (laBCC) or metastatic BCC (mBCC) | 350 mg every 3 weeks | Until disease progression, unacceptable toxicity, or up to 24 months.
Adults with non-small cell lung cancer (NSCLC) [Single-agent or in combination with platinum-based chemotherapy] | 350 mg every 3 weeks | Until disease progression or unacceptable toxicity.

2.3 Dosage Modifications for Adverse Reactions

No dose reduction for LIBTAYO is recommended. In general, withhold LIBTAYO for severe (Grade 3) immune-mediated adverse reactions. Permanently discontinue LIBTAYO for life-threatening (Grade 4) immune-mediated adverse reactions, recurrent severe (Grade 3) immune-mediated reactions that require systemic immunosuppressive treatment, or an inability to reduce corticosteroid dose to 10 mg or less of prednisone equivalent per day within 12 weeks of initiating steroids.

Dosage modifications for LIBTAYO for adverse reactions that require management different from these general guidelines are summarized in Table 2.

Table 2: Recommended Dosage Modifications for Adverse Reactions
Adverse Reaction | Severity [Based on National Cancer Institute Common Terminology Criteria for Adverse Events, Version 4.0] | Dosage Modifications
Immune-Mediated Adverse Reactions [see Warnings and Precautions (5.1)]
Pneumonitis | Grade 2 | Withhold [Resume in patients with complete or partial resolution (Grade 0 to 1) after corticosteroid taper. Permanently discontinue if no complete or partial resolution within 12 weeks of initiating steroids or inability to reduce prednisone to less than 10 mg per day (or equivalent) within 12 weeks of initiating steroids.]
Pneumonitis | Grade 3 or 4 | Permanently discontinue
Colitis | Grade 2 or 3 | Withhold
Colitis | Grade 4 | Permanently discontinue
Hepatitis with no tumor involvement of the liver | AST or ALT increases to more than 3 and up to 8 times ULN or Total bilirubin increases to more than 1.5 and up to 3 times the ULN | Withhold
Hepatitis with no tumor involvement of the liver | AST or ALT increases to more than 8 times the ULN or Total bilirubin increases to more than 3 times the ULN | Permanently discontinue
Hepatitis with tumor involvement of the liver [If AST and ALT are less than or equal to ULN at baseline, withhold or permanently discontinue LIBTAYO based on recommendations for hepatitis with no liver involvement] | Baseline AST or ALT is more than 1 and up to 3 times ULN and increases to more than 5 and up to 10 times ULN or Baseline AST or ALT is more than 3 and up to 5 times ULN and increases to more than 8 and up to 10 times ULN | Withhold
Hepatitis with tumor involvement of the liver [If AST and ALT are less than or equal to ULN at baseline, withhold or permanently discontinue LIBTAYO based on recommendations for hepatitis with no liver involvement] | AST or ALT increases to more than 10 times ULN or Total bilirubin increases to more than 3 times ULN | Permanently discontinue
Endocrinopathies | Grade 3 or 4 | Withhold until clinically stable or permanently discontinue depending on severity
Nephritis with Renal Dysfunction | Grade 2 or 3 increased blood creatinine | Withhold
Nephritis with Renal Dysfunction | Grade 4 increased blood creatinine | Permanently discontinue
Exfoliative Dermatologic Conditions | Suspected SJS, TEN, or DRESS | Withhold
Exfoliative Dermatologic Conditions | Confirmed SJS, TEN, or DRESS | Permanently discontinue
Myocarditis | Grade 2, 3 or 4 | Permanently discontinue
Neurological Toxicities | Grade 2 | Withhold
Neurological Toxicities | Grade 3 or 4 | Permanently discontinue
Other Adverse Reactions
Infusion-related reactions [see Warnings and Precautions (5.2)] | Grade 1 or 2 | Interrupt or slow the rate of infusion
Infusion-related reactions [see Warnings and Precautions (5.2)] | Grade 3 or 4 | Permanently discontinue
ALT=alanine aminotransferase, AST=aspartate aminotransferase, ULN=upper limit of normal, SJS=Stevens-Johnson Syndrome, TEN=toxic epidermal necrolysis, DRESS=Drug Rash with Eosinophilia and Systemic Symptoms

2.4 Preparation and Administration

- Visually inspect for particulate matter and discoloration prior to administration. LIBTAYO is a clear to slightly opalescent, colorless to pale yellow solution that may contain trace amounts of translucent to white particles. Discard the vial if the solution is cloudy, discolored or contains extraneous particulate matter other than trace amounts of translucent to white particles.

Preparation

- Do not shake the vial(s).
- Withdraw the required volume from the vial(s) of LIBTAYO and transfer into an intravenous (IV) bag containing 0.9% Sodium Chloride Injection, USP or 5% Dextrose Injection, USP to a final concentration between 1 mg/mL to 20 mg/mL.
- Mix diluted solution by gentle inversion. Do not shake.
- Discard any unused portion left in the vial(s).

Storage of Diluted Solution

- Store at
  - room temperature up to 25°C (77°F) for no more than 8 hours from the time of preparation to the end of the infusion or
  - under refrigeration at 2°C to 8°C (36°F to 46°F) for no more than 10 days from the time of preparation to the end of infusion.
- Allow the diluted solution to come to room temperature prior to administration.
- Do not freeze.

Administration

- Administer by intravenous infusion over 30 minutes through an intravenous line containing a sterile, in-line or add-on 0.2-micron to 5-micron filter.

3 DOSAGE FORMS AND STRENGTHS

Injection: 350 mg/7 mL (50 mg/mL), clear to slightly opalescent, colorless to pale yellow solution that may contain trace amounts of translucent to white particles in a single-dose vial.

4 CONTRAINDICATIONS

None.

5 WARNINGS AND PRECAUTIONS

5.1 Severe and Fatal Immune-Mediated Adverse Reactions

LIBTAYO is a monoclonal antibody that belongs to a class of drugs that bind to either the programmed death receptor-1 (PD-1) or PD-ligand 1 (PD-L1), blocking the PD-1/PD-L1 pathway, thereby removing inhibition of the immune response, potentially breaking peripheral tolerance and inducing immune-mediated adverse reactions. Important immune-mediated adverse reactions listed under Warnings and Precautions may not include all possible severe and fatal immune-mediated reactions.

The incidence and severity of immune-mediated adverse reactions were similar when LIBTAYO was administered as a single agent or in combination with chemotherapy.

Immune-mediated adverse reactions, which may be severe or fatal, can occur in any organ system or tissue. Immune-mediated adverse reactions can occur at any time after starting PD-1/PD-L1 blocking antibody. While immune-mediated adverse reactions usually manifest during treatment with PD-1/PD-L1 blocking antibodies, immune-mediated adverse reactions can also manifest after discontinuation of PD-1/PD-L1 blocking antibodies. Immune-mediated adverse reactions affecting more than one body system can occur simultaneously.

Early identification and management of immune‐mediated adverse reactions are essential to ensure safe use of PD-1/PD-L1 blocking antibodies. Monitor closely for symptoms and signs that may be clinical manifestations of underlying immune-mediated adverse reactions. Evaluate liver enzymes, creatinine, and thyroid function at baseline and periodically during treatment. In cases of suspected immune-mediated adverse reactions, initiate appropriate workup to exclude alternative etiologies, including infection. Institute medical management promptly, including specialty consultation as appropriate.

Withhold or permanently discontinue LIBTAYO depending on severity [see Dosage and Administration (2.3)]. In general, if LIBTAYO requires interruption or discontinuation, administer systemic corticosteroid therapy (1 to 2 mg/kg/day prednisone or equivalent) until improvement to Grade 1 or less. Upon improvement to Grade 1 or less, initiate corticosteroid taper and continue to taper over at least 1 month. Consider administration of other systemic immunosuppressants in patients whose immune-mediated adverse reactions are not controlled with corticosteroids.

Toxicity management guidelines for adverse reactions that do not necessarily require systemic steroids (e.g., endocrinopathies and dermatologic reactions) are discussed below.

Immune-Mediated Pneumonitis

LIBTAYO can cause immune-mediated pneumonitis. The definition of immune-mediated pneumonitis included the required use of systemic corticosteroids or other immunosuppressants and the absence of a clear alternate etiology. In patients treated with other PD-1/PD-L1 blocking antibodies the incidence of pneumonitis is higher in patients who have received prior thoracic radiation.

Immune-mediated pneumonitis occurred in 2.6% (33/1281) of patients receiving LIBTAYO, including Grade 4 (0.3%), Grade 3 (0.6%), and Grade 2 (1.6%) adverse reactions. Pneumonitis led to permanent discontinuation of LIBTAYO in 1.3% of patients and withholding of LIBTAYO in 1.4% of the patients.

Systemic corticosteroids were required in all patients with pneumonitis. Pneumonitis resolved in 61% of the 33 patients. Of the 18 patients in whom LIBTAYO was withheld for pneumonitis, 10 reinitiated LIBTAYO after symptom improvement; of these, 4/10 (40%) had recurrence of pneumonitis.

Immune-Mediated Colitis

LIBTAYO can cause immune-mediated colitis. The definition of immune-mediated colitis included the required use of systemic corticosteroids or other immunosuppressants and the absence of a clear alternate etiology. The primary component of the immune-mediated colitis was diarrhea. Cytomegalovirus (CMV) infection/reactivation has been reported in patients with corticosteroid-refractory immune-mediated colitis treated with PD-1/PD-L1 blocking antibodies. In cases of corticosteroid refractory colitis, consider repeating infectious workup to exclude alternative etiologies.

Immune-mediated colitis occurred in 2% (25/1281) of patients receiving LIBTAYO, including Grade 3 (0.8%) and Grade 2 (0.9%) adverse reactions. Colitis led to permanent discontinuation of LIBTAYO in 0.4% of patients and withholding of LIBTAYO in 1.2% of patients.

Systemic corticosteroids were required in all patients with colitis. Colitis resolved in 56% of the 25 patients. Of the 16 patients in whom LIBTAYO was withheld for colitis, 6 reinitiated LIBTAYO after symptom improvement; of these, 4/6 (67%) had recurrence of colitis.

Immune-Mediated Hepatitis

LIBTAYO can cause immune-mediated hepatitis. The definition of immune-mediated hepatitis included the required use of systemic corticosteroids or other immunosuppressants and the absence of a clear alternate etiology.

Immune-mediated hepatitis occurred in 2.4% (31/1281) of patients receiving LIBTAYO, including fatal (< 0.1%), Grade 4 (0.3%), Grade 3 (1.6%), and Grade 2 (0.2%) adverse reactions. Hepatitis led to permanent discontinuation of LIBTAYO in 1.4% of patients and withholding of LIBTAYO in 0.7% of patients.

Systemic corticosteroids were required in all patients with hepatitis. Thirteen percent (13%) of these patients (4/31) required additional immunosuppression with mycophenolate. Hepatitis resolved in 39% of the 31 patients. Of the 9 patients in whom LIBTAYO was withheld for hepatitis, 5 patients reinitiated LIBTAYO after symptom improvement; of these, 1/5 (20%) had recurrence of hepatitis.

Immune-Mediated Endocrinopathies

Adrenal Insufficiency

LIBTAYO can cause primary or secondary adrenal insufficiency. For Grade 2 or higher adrenal insufficiency, initiate symptomatic treatment, including hormone replacement as clinically indicated. Withhold LIBTAYO depending on severity [see Dosage and Administration (2.3)].

Adrenal insufficiency occurred in 0.5% (6/1281) of patients receiving LIBTAYO, including Grade 3 (0.5%) adverse reactions. Adrenal insufficiency led to permanent discontinuation of LIBTAYO in 1 (< 0.1%) patient. LIBTAYO was withheld in 1 (< 0.1%) patient due to adrenal insufficiency and not reinitiated. Systemic corticosteroids were required in 83% (5/6) patients with adrenal insufficiency; of these, the majority remained on systemic corticosteroids. Adrenal insufficiency resolved in 17% of the 6 patients.

Hypophysitis

LIBTAYO can cause immune-mediated hypophysitis. Hypophysitis can present with acute symptoms associated with mass effect such as headache, photophobia, or visual field defects. Hypophysitis can cause hypopituitarism. Initiate hormone replacement as clinically indicated. Withhold or permanently discontinue LIBTAYO depending on severity [see Dosage and Administration (2.3)].

Hypophysitis occurred in 0.5% (7/1281) of patients receiving LIBTAYO, including Grade 3 (0.2%) and Grade 2 (0.3%) adverse reactions. Hypophysitis led to permanent discontinuation of LIBTAYO in 1 (< 0.1%) patient and withholding of LIBTAYO in 2 (0.2%) patients. Systemic corticosteroids were required in 86% (6/7) patients with hypophysitis. Hypophysitis resolved in 14% of the 7 patients. Of the 2 patients in whom LIBTAYO was withheld for hypophysitis, none of the patients reinitiated.

Thyroid Disorders

LIBTAYO can cause immune-mediated thyroid disorders. Thyroiditis can present with or without endocrinopathy. Hypothyroidism can follow hyperthyroidism. Initiate hormone replacement or medical management as clinically indicated. Withhold or permanently discontinue LIBTAYO depending on severity [see Dosage and Administration (2.3)].

Thyroiditis: Thyroiditis occurred in 0.6% (8/1281) of patients receiving LIBTAYO, including Grade 2 (0.3%) adverse reactions. No patient discontinued LIBTAYO due to thyroiditis. Thyroiditis led to withholding of LIBTAYO in 1 (< 0.1%) patient. Systemic corticosteroids were not required in any patient with thyroiditis. Thyroiditis resolved in 13% of the 8 patients.

Blood thyroid stimulating hormone increased and blood thyroid stimulating hormone decreased have also been reported.

Hyperthyroidism: Hyperthyroidism occurred in 3% (39/1281) of patients receiving LIBTAYO, including Grade 3 (< 0.1%) and Grade 2 (0.9%) adverse reactions. No patient discontinued treatment due to hyperthyroidism. Hyperthyroidism led to withholding of LIBTAYO in 7 (0.5%) patients.

Systemic corticosteroids were required in 8% (3/39) of patients with hyperthyroidism. Hyperthyroidism resolved in 56% of the 39 patients. Of the 7 patients in whom LIBTAYO was withheld for hyperthyroidism, 2 patients reinitiated LIBTAYO after symptom improvement; of these, none had recurrence of hyperthyroidism.

Hypothyroidism: Hypothyroidism occurred in 7% (87/1281) of patients receiving LIBTAYO, including Grade 3 (< 0.1%) and Grade 2 (6%) adverse reactions. Hypothyroidism led to permanent discontinuation of LIBTAYO in 3 (0.2%) patients. Hypothyroidism led to withholding of LIBTAYO in 9 (0.7%) patients.

Systemic corticosteroids were required in 1.1% (1/87) of patients. Hypothyroidism resolved in 6% of the 87 patients. The majority of patients with hypothyroidism required long-term thyroid hormone replacement.

Of the 9 patients in whom LIBTAYO was withheld for hypothyroidism, 1 reinitiated LIBTAYO after symptom improvement and did not have recurrence of hypothyroidism.

Type 1 Diabetes Mellitus, which can present with diabetic ketoacidosis

Monitor patients for hyperglycemia or other signs and symptoms of diabetes. Initiate treatment with insulin as clinically indicated. Withhold LIBTAYO depending on severity [see Dosage and Administration (2.3)].

Type 1 diabetes mellitus occurred in < 0.1% (1/1281) of patients (Grade 4). No patient discontinued treatment due to type 1 diabetes mellitus. Type 1 diabetes mellitus led to withholding of LIBTAYO in 0.1% of patients, treatment was reinitiated after symptom improvement. Patient received long-term insulin therapy.

Immune-Mediated Nephritis with Renal Dysfunction

LIBTAYO can cause immune-mediated nephritis. The definition of immune-mediated nephritis included the required use of systemic corticosteroids or other immunosuppressants and the absence of a clear alternate etiology.

Immune-mediated nephritis occurred in 0.7% (9/1281) patients receiving LIBTAYO, including fatal (< 0.1%), Grade 3 (< 0.1%) and Grade 2 (0.5%) adverse reactions. Nephritis led to permanent discontinuation of LIBTAYO in 0.2% of patients and withholding of LIBTAYO in 0.4% of patients.

Systemic corticosteroids were required in all patients with nephritis. Nephritis resolved in 78% of the 9 patients. Of the 5 patients in whom LIBTAYO was withheld for nephritis, 4 reinitiated LIBTAYO after symptom improvement; of these, 1/4 (25%) had recurrence of nephritis.

Immune-Mediated Dermatologic Adverse Reactions

LIBTAYO can cause immune-mediated rash or dermatitis. The definition of immune-mediated dermatologic adverse reaction included the required use of systemic corticosteroids or other immunosuppressants and the absence of a clear alternate etiology. Exfoliative dermatitis, including Stevens-Johnson Syndrome (SJS), toxic epidermal necrolysis (TEN), and DRESS (Drug Rash with Eosinophilia and Systemic Symptoms), has occurred with PD-1/PD-L1 blocking antibodies. Topical emollients and/or topical corticosteroids may be adequate to treat mild to moderate non-exfoliative rashes. Withhold or permanently discontinue LIBTAYO depending on severity [see Dosage and Administration (2.3)].

Immune-mediated dermatologic adverse reactions occurred in 1.9% (24/1281) of patients receiving LIBTAYO, including Grade 3 (0.9%) and Grade 2 (0.8%) adverse reactions. Dermatologic adverse reactions led to permanent discontinuation of LIBTAYO in 0.2% of patients and withholding of LIBTAYO in 1.3% of patients.

Systemic corticosteroids were required in all patients with immune-mediated dermatologic adverse reactions. Immune-mediated dermatologic adverse reactions resolved in 71% of the 24 patients. Of the 17 patients in whom LIBTAYO was withheld for dermatologic adverse reaction, 13 reinitiated LIBTAYO after symptom improvement; of these 5/13 (38%) had recurrence of the dermatologic adverse reaction.

Other Immune-Mediated Adverse Reactions

The following clinically significant immune-mediated adverse reactions occurred at an incidence of <1% in 1281 patients who received LIBTAYO or were reported with the use of other PD-1/PD-L1 blocking antibodies. Severe or fatal cases have been reported for some of these adverse reactions.

Cardiac/Vascular: Myocarditis, pericarditis, vasculitis

Nervous System: Meningitis, encephalitis, myelitis and demyelination, myasthenic syndrome/myasthenia gravis (including exacerbation), Guillain-Barre syndrome, nerve paresis, autoimmune neuropathy

Ocular: Uveitis, iritis, and other ocular inflammatory toxicities. Some cases can be associated with retinal detachment. Various grades of visual impairment to include blindness can occur. If uveitis occurs in combination with other immune-mediated adverse reactions, consider a Vogt-Koyanagi-Harada like syndrome, as this may require treatment with systemic steroids to reduce the risk of permanent vision loss

Gastrointestinal: Pancreatitis to include increases in serum amylase and lipase levels, gastritis, duodenitis, stomatitis

Musculoskeletal and Connective Tissue: Myositis/polymyositis/dermatomyositis, rhabdomyolysis and associated sequelae including renal failure, arthritis, polymyalgia rheumatica

Endocrine: Hypoparathyroidism

Other (Hematologic/Immune): Hemolytic anemia, aplastic anemia, hemophagocytic lymphohistiocytosis, systemic inflammatory response syndrome, histiocytic necrotizing lymphadenitis (Kikuchi lymphadenitis), sarcoidosis, immune thrombocytopenia, solid organ transplant rejection, other transplant (including corneal graft) rejection

5.2 Infusion-Related Reactions

Severe or life-threatening infusion-related reactions occurred in 0.2% of patients receiving LIBTAYO as a single agent. Monitor patients for signs and symptoms of infusion-related reactions. Common symptoms of infusion-related reaction include nausea, pyrexia, and vomiting.

Interrupt or slow the rate of infusion or permanently discontinue LIBTAYO based on severity of reaction [see Dosage and Administration (2.3)].

5.3 Complications of Allogeneic HSCT

Fatal and other serious complications can occur in patients who receive allogeneic hematopoietic stem cell transplantation (HSCT) before or after being treated with a PD-1/PD-L1 blocking antibody. Transplant-related complications include hyperacute graft-versus-host-disease (GVHD), acute GVHD, chronic GVHD, hepatic veno-occlusive disease (VOD) after reduced intensity conditioning, and steroid-requiring febrile syndrome (without an identified infectious cause). These complications may occur despite intervening therapy between PD-1/PD-L1 blockade and allogeneic HSCT.

Follow patients closely for evidence of transplant-related complications and intervene promptly. Consider the benefit versus risks of treatment with a PD-1/PD-L1 blocking antibody prior to or after an allogeneic HSCT.

5.4 Embryo-Fetal Toxicity

Based on its mechanism of action, LIBTAYO can cause fetal harm when administered to a pregnant woman. Animal studies have demonstrated that inhibition of the PD-1/PD-L1 pathway can lead to increased risk of immune-mediated rejection of the developing fetus resulting in fetal death. Advise women of the potential risk to a fetus. Advise females of reproductive potential to use effective contraception during treatment with LIBTAYO and for at least 4 months after the last dose [see Use in Specific Populations (8.1, 8.3)].

6 ADVERSE REACTIONS

The following serious adverse reactions are described elsewhere in the labeling.

- Severe and Fatal Immune-Mediated Adverse Reactions [see Warnings and Precautions (5.1)]
- Infusion-Related Reactions [see Warnings and Precautions (5.2)]
- Complications of Allogeneic HSCT [see Warnings and Precautions (5.3)]

6.1 Clinical Trials Experience

Because clinical trials are conducted under widely varying conditions, adverse reaction rates observed in the clinical trials of a drug cannot be directly compared to rates in the clinical trials of another drug and may not reflect the rates observed in practice.

The data described in Warnings and Precautions reflect exposure to LIBTAYO as a single agent in 1281 patients with advanced cancers in three open-label, single-arm, multicohort studies, and two open-label randomized multi-center studies. These studies included 384 patients with advanced CSCC (Studies 1540 and 1423), 138 patients with advanced BCC (Study 1620), 355 patients with NSCLC (Study 1624), and 404 patients with other advanced solid tumors. LIBTAYO was administered intravenously at doses of 3 mg/kg every 2 weeks (n=235), 350 mg every 3 weeks (n=1014), or other doses (n=32). Among the 1281 patients, 53% were exposed for 6 months or longer and 26% were exposed for one year or longer. In this pooled safety population, the most common adverse reactions (≥15%) were fatigue, musculoskeletal pain, rash, diarrhea, and anemia. The most common Grade 3-4 laboratory abnormalities (≥2%) were lymphopenia, anemia, hyponatremia, hypophosphatemia, increased aspartate aminotransferase, hypokalemia, hyperkalemia, and increased alanine aminotransferase.

The data below also reflect exposure to LIBTAYO as a single agent (either 350 mg every 3 weeks for 12 weeks followed by 700 mg every 6 weeks for 36 weeks or 350 mg every 3 weeks for 48 weeks) in the adjuvant setting in 205 patients with CSCC at high risk of recurrence after treatment with surgery and radiation (C-POST study), and LIBTAYO 350 mg every 3 weeks in combination with platinum-based chemotherapy in 312 patients with NSCLC enrolled in a randomized, active controlled trial (Study 16113).

Cutaneous Squamous Cell Carcinoma (CSCC)

Study 1540

The safety of LIBTAYO was evaluated in 358 patients with advanced CSCC (metastatic or locally advanced disease) in Study 1540 [see Clinical Studies (14.1)]. Of these 358 patients, 213 had mCSCC (nodal or distant) and 145 had laCSCC. Patients received LIBTAYO 3 mg/kg every 2 weeks (n=137) or 350 mg every 3 weeks (n=221) as an intravenous infusion until disease progression, unacceptable toxicity, or completion of planned treatment. The median duration of exposure was 40 weeks (1 week to 109 weeks).

Serious adverse reactions occurred in 41% of patients. Serious adverse reactions that occurred in at least 2% of patients were pneumonia (3.6%), skin infection (3.6%), and pneumonitis (2.8%). Fatal adverse reactions occurred in 5% of patients who received LIBTAYO, including deaths due to infections (2.2%).

Permanent discontinuation due to an adverse reaction occurred in 12% of patients. Adverse reactions resulting in permanent discontinuation in at least 2 patients were pneumonitis, rash, confusional state, general physical health deterioration, hemorrhage, liver function test abnormalities, and musculoskeletal pain.

Dosage interruptions of LIBTAYO due to an adverse reaction occurred in 36% of patients. Adverse reactions which required dosage interruption in ≥2% of patients included diarrhea, infusion-related reaction, upper respiratory tract infection, liver function test abnormalities, musculoskeletal pain, pneumonitis, and rash.

The most common (≥20%) adverse reactions were fatigue, rash, musculoskeletal pain, diarrhea, pruritus, and nausea. The most common Grade 3 or 4 adverse reactions (≥2%) were hypertension, skin infection, pneumonia, anemia, fatigue, musculoskeletal pain, and pneumonitis. The most common (≥4%) Grade 3 or 4 laboratory abnormalities worsening from baseline were lymphopenia, hyponatremia, anemia, and hypophosphatemia.

Table 3 summarizes the adverse reactions that occurred in ≥10% of patients and Table 4 summarizes Grade 3 or 4 laboratory abnormalities worsening from baseline in ≥1% of patients receiving LIBTAYO.

Table 3: Adverse Reactions in ≥10% of Patients with Advanced CSCC Receiving LIBTAYO in Study 1540
Adverse Reactions | LIBTAYO N = 358
Adverse Reactions | All Grades % | Grades 3-4 %
General and Administration Site
Fatigue [Fatigue is a composite term that includes fatigue and asthenia] | 38 | 2.2
Skin and Subcutaneous Tissue
Rash [Rash is a composite term that includes rash, rash maculo-papular, dermatitis, erythema, eczema, dermatitis bullous, rash erythematous, dermatitis acneiform, psoriasis, dermatitis contact, blister, pemphigoid, rash papular, hand dermatitis, skin exfoliation, autoimmune dermatitis, rash pruritic, rash macular, rash pustular, urticaria, dermatitis atopic, drug eruption, eczema asteatotic, skin reaction, dermatitis psoriasiform, eczema nummular, exfoliative rash, and immune-mediated dermatitis] | 34 | 1.7
Pruritus [Pruritus is a composite term that includes pruritus and pruritus allergic] | 22 | 0.3
Actinic keratosis | 10 | 0
Musculoskeletal and Connective Tissue
Musculoskeletal pain [Musculoskeletal pain is a composite term that includes arthralgia, back pain, myalgia, polyarthritis, pain in extremity, neck pain, non-cardiac chest pain, arthritis, musculoskeletal chest pain, musculoskeletal pain, musculoskeletal stiffness, bone pain, immune-mediated arthritis, and spinal pain] | 33 | 2.5
Gastrointestinal
Diarrhea [Diarrhea is a composite term that includes diarrhea, colitis, and autoimmune colitis] | 26 | 1.1
Nausea | 21 | 0
Constipation | 13 | 0.3
Vomiting [Vomiting is a composite term that includes hematemesis and vomiting] | 11 | 0.6
Infections and infestations
Upper respiratory tract infection [Upper respiratory tract infection is a composite term that includes upper respiratory tract infection, nasopharyngitis, sinusitis, influenza-like illness, rhinitis, influenza, viral upper respiratory tract infection, respiratory tract infection, influenza A virus test positive, and pharyngitis] | 14 | 1.1
Skin infection [Skin infection is a composite term that includes skin infection, cellulitis, fungal skin infection, and staphylococcal skin infection] | 11 | 4.5
Respiratory
Cough [Cough is a composite term that includes cough, productive cough, and upper airway cough syndrome] | 12 | 0
Metabolism and Nutrition
Decreased appetite | 11 | 0.6
Nervous system disorders
Headache [Headache is a composite term that includes headache, sinus headache, and migraine] | 10 | 0
Dizziness [Dizziness is a composite term that includes dizziness, vertigo, vertigo positional, and dizziness postural] | 10 | 0.3
Toxicity was graded per National Cancer Institute Common Terminology Criteria for Adverse Events (NCI CTCAE) v.4.03

Table 4: Grade 3 or 4 Laboratory Abnormalities Worsening from Baseline in ≥1% of Patients with Advanced CSCC Receiving LIBTAYO in Study 1540
Laboratory Abnormality | Grade 3-4 (%) [Percentages are based on the number of patients with at least 1 post-baseline value available for that parameter]
Hematology
Lymphopenia | 7.0
Anemia | 4.1
Electrolytes
Hyponatremia | 4.9
Hypophosphatemia | 4.1
Hypercalcemia | 2.0
Hypokalemia | 1.5
Coagulation
Increased INR | 2.9
Chemistry
Increased aspartate aminotransferase | 1.5
Hypoalbuminemia | 1.2
Toxicity graded per NCI CTCAE v. 4.03

Study 1423

In 26 patients with advanced CSCC treated with LIBTAYO in Study 1423 [see Clinical Studies (14.1)], safety data were consistent with those described above from Study 1540.

Adjuvant treatment of CSCC at high risk of recurrence

C-POST study

The safety of LIBTAYO was evaluated in patients with CSCC at high-risk of recurrence after surgery and radiation in the C-POST study [see Clinical Studies (14.1)].

Patients were assigned to receive:

- LIBTAYO 350 mg (n=140) or placebo (n=140) intravenously every 3 weeks for 12 weeks, followed by 700 mg LIBTAYO or placebo intravenously every 6 weeks for an additional 36 weeks, or
- LIBTAYO 350 mg every 3 weeks (n=65) or placebo (n=64) for up to 48 weeks.

Treatment continued until disease recurrence, unacceptable toxicity, or up to 48 weeks.

The median duration of exposure was 48 weeks (range: 3 weeks to 52 weeks) in LIBTAYO-treated patients.

Serious adverse reactions occurred in 18% of patients who received LIBTAYO. Serious adverse reactions that occurred in ≥1% of patients in the LIBTAYO arm were pneumonia (1.5%), rash (1.5%), diarrhea (1.5%), adrenal insufficiency (1%), and arrhythmia (1%).

Permanent discontinuation due to an adverse reaction occurred in 10% of patients who received LIBTAYO. Adverse reactions resulting in permanent discontinuation in ≥1% of patients were alanine aminotransferase increased, aspartate aminotransferase increased, blood alkaline phosphatase increased, and adrenal insufficiency.

Dosage interruptions due to an adverse reaction occurred in 22% of patients who received LIBTAYO. Adverse reactions leading to interruptions in ≥1% of patients included COVID-19, diarrhea, alanine aminotransferase increased, urinary tract infection, upper respiratory tract infection, aspartate aminotransferase increased, edema, dyspnea, pneumonitis, pneumonia, and rash.

Table 5 summarizes the adverse reactions that occurred in ≥10% of patients and Table 6 summarizes Grade 3 or 4 laboratory abnormalities worsening from baseline in ≥1% of patients receiving LIBTAYO.

Table 5: Adverse Reactions in ≥10% of Patients with CSCC at High Risk of Recurrence in the Adjuvant Setting Receiving LIBTAYO with a Difference Between Arms of ≥3% Compared to Placebo in C-POST study
Adverse reactions [Toxicity graded per NCI CTCAE v. 5.] | LIBTAYO N=205 |  | Placebo N=204
Adverse reactions [Toxicity graded per NCI CTCAE v. 5.] | All Grades % | Grades 3-4 % | All Grades % | Grades 3-4 %
Skin and subcutaneous tissue disorders
Rash [Includes multiple related terms] | 37 | 2 | 21 | 0
Pruritus | 16 | 0.5 | 12 | 0
Endocrine disorders
Hypothyroidism | 12 | 0.5 | 2.9 | 0

Table 6: Laboratory Abnormalities Worsening from Baseline in ≥1% of Patients with CSCC at High Risk of Recurrence in the Adjuvant Setting Receiving LIBTAYO in C-POST Study
Laboratory Abnormality | LIBTAYO | Placebo
Laboratory Abnormality | Grade 3-4 (%) [The denominator used to calculate the rate varied from 201 to 203 based on the number of patients with a baseline value and at least one post-treatment value.]
Hematology
Lymphocyte count decreased | 6 | 3
Chemistry
Alanine aminotransferase increased | 3.9 | 0
Aspartate aminotransferase increased | 3 | 0.5
Alkaline phosphatase increased | 1.5 | 0
Albumin decreased | 1 | 0
Electrolytes
Calcium decreased | 1 | 1
Potassium decreased | 1 | 0.5
Toxicity graded per NCI CTCAE v. 5

Basal Cell Carcinoma (BCC)

The safety of LIBTAYO was evaluated in 138 patients with advanced BCC (mBCC N=54, laBCC N=84) in an open-label, single-arm trial (Study 1620) [see Clinical Studies (14.2)]. Patients received LIBTAYO 350 mg every 3 weeks as an intravenous infusion for up to 93 weeks or until disease progression or unacceptable toxicity. The median duration of exposure was 45 weeks (range: 2.1 weeks to 98 weeks).

Serious adverse reactions occurred in 34% of patients. Serious adverse reactions that occurred in > 1.5% were diarrhea (3.6%), urinary tract infection (3.6%), pneumonia (2.9%), and hemorrhage (2.2%). Fatal adverse reactions occurred in 4.3% of patients who received LIBTAYO, including acute kidney injury (0.7%) and cachexia worsening due to colitis (0.7%).

Permanent discontinuation of LIBTAYO due to an adverse reaction occurred in 14% of patients. Adverse reactions resulting in permanent discontinuation of LIBTAYO in at least 2 patients were diarrhea, acute kidney injury, general physical health deterioration, and hepatitis.

Dosage interruptions of LIBTAYO due to an adverse reaction occurred in 40% of patients. Adverse reactions which required dosage interruptions in > 2% of patients included diarrhea, musculoskeletal pain, acute kidney injury, fatigue, fall, headache, infusion-related reaction, hemorrhage, pneumonitis, upper respiratory tract infection, and urinary tract infection.

The most common adverse reactions reported in at least 15% of patients were fatigue, musculoskeletal pain, diarrhea, rash, upper respiratory tract infection, pruritus, hemorrhage, and hypertension.

The most common Grade 3 or 4 adverse reactions (> 2%) were hypertension, diarrhea, fatigue, musculoskeletal pain, hypokalemia, hyponatremia, pneumonia, urinary tract infection, visual impairment, and weight decreased. The most common (> 2%) laboratory abnormalities worsening from baseline to Grade 3 or 4 were lymphopenia and hyponatremia.

Table 7 summarizes the adverse reactions that occurred in ≥10% of patients and Table 8 summarizes Grade 3 or 4 laboratory abnormalities worsening from baseline in ≥1% of patients receiving LIBTAYO.

Table 7: Adverse Reactions in ≥10% of Patients with Advanced BCC Receiving LIBTAYO in Study 1620
Adverse Reactions | LIBTAYO N = 138
Adverse Reactions | All Grades % | Grades 3-4 %
General disorders and administration site conditions
Fatigue [Fatigue is a composite term that includes fatigue, asthenia, and malaise] | 50 | 4.3
Edema [Edema is a composite term that includes peripheral edema, peripheral swelling, and face swelling] | 10 | 0.7
Musculoskeletal and connective tissue disorders
Musculoskeletal pain [Musculoskeletal pain is a composite term that includes arthralgia, back pain, pain in extremity, myalgia, neck pain, non-cardiac chest pain, arthritis, musculoskeletal chest pain, musculoskeletal stiffness, musculoskeletal discomfort, and spinal pain] | 36 | 2.9
Gastrointestinal disorders
Diarrhea [Diarrhea is a composite term that includes diarrhea, colitis, autoimmune colitis, and enterocolitis] | 33 | 4.3
Nausea | 13 | 0.7
Abdominal pain [Abdominal pain is a composite term that includes abdominal pain, abdominal pain upper, abdominal pain lower, and gastrointestinal pain] | 12 | 1.4
Constipation | 12 | 0.7
Skin and subcutaneous tissue disorders
Rash [Rash is a composite term that includes rash maculo-papular, eczema, rash, dermatitis, erythema, dermatitis acneiform, rash pruritic, rash pustular, dermatitis bullous, dyshidrotic eczema, pemphigoid, rash erythematous, urticaria, nodular rash, and skin exfoliation] | 30 | 0.7
Pruritus | 19 | 0
Infections and infestations
Upper respiratory tract infection [Upper respiratory tract infection is a composite term that includes upper respiratory tract infection, influenza-like illness, nasopharyngitis, rhinitis, sinusitis, viral rhinitis, pharyngitis, laryngitis, respiratory tract infection, influenza, viral upper respiratory tract infection, and influenza A virus test positive] | 22 | 0
Urinary tract infection [Urinary tract infection is a composite term that includes urinary tract infection, cystitis, and urosepsis] | 13 | 2.2
Vascular disorders
Hemorrhage [Hemorrhage is a composite term that includes tumor hemorrhage, hematuria, epistaxis, eye hemorrhage, hemoptysis, hemorrhage intracranial, hemorrhagic diathesis, postmenopausal hemorrhage, rectal hemorrhage, skin hemorrhage, skin neoplasm bleeding, ulcer hemorrhage, vaginal hemorrhage, wound hemorrhage, and subcutaneous hematoma] | 18 | 0.7
Hypertension [Hypertension is a composite term that includes hypertension, blood pressure increased, and hypertensive crisis] | 17 | 9
Metabolism and nutrition disorders
Decreased appetite | 14 | 1.4
Blood and lymphatic system disorders
Anemia | 14 | 0.7
Respiratory, thoracic, and mediastinal disorders
Dyspnea [Dyspnea is a composite term that includes dyspnea and dyspnea exertional] | 14 | 0
Renal and urinary disorders
Acute kidney injury [Acute kidney injury is a composite term that includes blood creatinine increased, acute kidney injury, renal failure, renal impairment, glomerular filtration rate decreased, and nephropathy toxic] | 14 | 0
Nervous system disorders
Headache | 13 | 1.4
Dizziness [Dizziness is a composite term that includes dizziness and vertigo] | 12 | 0
Peripheral neuropathy [Peripheral neuropathy is a composite term that includes paresthesia, dysesthesia, hypoesthesia, peripheral motor neuropathy, burning sensation, neuralgia, and peripheral sensory neuropathy] | 11 | 0
Endocrine disorders
Hypothyroidism [Hypothyroidism is a composite term that includes hypothyroidism, blood thyroid stimulating hormone increased, and immune-mediated hypothyroidism] | 12 | 0
Investigations
Liver function test abnormalities [Liver function test abnormalities is a composite term that includes alanine aminotransferase increased, aspartate aminotransferase increased, bilirubin conjugated increased, blood alkaline phosphatase increased, blood bilirubin increased, and gamma-glutamyl transferase increased] | 10 | 1.4
Toxicity was graded per National Cancer Institute Common Terminology Criteria for Adverse Events (NCI CTCAE) v.4.03

Table 8: Grade 3 or 4 Laboratory Abnormalities Worsening from Baseline in ≥1% of Patients with Advanced BCC Receiving LIBTAYO in Study 1620
Laboratory Abnormality | Grade 3-4 (%) [Percentages are based on the number of patients with at least 1 post-baseline value available for that parameter]
Hematology
Lymphopenia | 2.9
Electrolytes
Hyponatremia | 2.9
Hypokalemia | 1.5
Coagulation
Activated partial thromboplastin time prolonged | 1.9
Toxicity graded per NCI CTCAE v. 4.03

Non-Small Cell Lung Cancer (NSCLC)

First-line treatment of NSCLC with LIBTAYO in Combination with Platinum-based Chemotherapy

The safety of LIBTAYO in combination with platinum-based chemotherapy was evaluated in 465 patients with locally advanced or metastatic NSCLC in Study 16113 [see Clinical Studies (14.3)]. Patients received LIBTAYO 350 mg every 3 weeks plus platinum-based chemotherapy every 3 weeks for 4 cycles (n=312), or placebo every 3 weeks plus platinum-based chemotherapy every 3 weeks for 4 cycles (n=153).

Among patients who received LIBTAYO, 70% were exposed for 6 months or longer and 35% were exposed for greater than one year. The safety population characteristics were: median age of 63 years (25 to 82 years), 41% of patients 65 or older, 86% male, 86% White, 14% Asian, 86% had metastatic disease and 14% had locally advanced disease and Eastern Cooperative Oncology Group (ECOG) Performance Status (PS) of 0 (16%) and 1 (83%).

Serious adverse reactions occurred in 25% of patients. The most frequent serious adverse reactions that occurred in at least 2% of patients were pneumonia, anemia, and neutropenia. Fatal adverse reactions occurred in 6% of patients who received LIBTAYO in combination with chemotherapy, including death not otherwise specified (2.9%), sudden death (1.0%), acute hepatitis (0.3%), acute respiratory distress syndrome (0.3%), mesenteric artery thrombosis (0.3%), pneumonia (0.3%), pneumonitis (0.3%), and pulmonary hemorrhage (0.3%). LIBTAYO was permanently discontinued due to adverse reactions in 5% of patients. Adverse reactions resulting in permanent discontinuation in at least 2 patients were increased alanine aminotransferase and anemia.

Dosage interruptions of LIBTAYO due to an adverse reaction occurred in 33% of patients. Adverse reactions which required dosage interruptions in at least 2% of patients were anemia, pneumonia, neutropenia, thrombocytopenia, fatigue, COVID-19 infection, and pyrexia.

The most common (≥15%) adverse reactions were alopecia, musculoskeletal pain, nausea, fatigue, peripheral neuropathy, and decreased appetite. The most common Grade 3-4 laboratory abnormalities (≥2%) were anemia, neutropenia, lymphopenia, leukopenia, hyponatremia, thrombocytopenia, hyperglycemia, hypophosphatemia, increased alanine aminotransferase, hypocalcemia, hyperkalemia, hypermagnesemia, hypokalemia, and increased creatinine.

Table 9 summarizes the adverse reactions that occurred in ≥10% of patients and Table 10 summarizes Grade 3 or 4 laboratory abnormalities in patients receiving LIBTAYO and chemotherapy.

Table 9: Adverse Reactions in ≥10% of Patients with Locally Advanced or Metastatic NSCLC Receiving LIBTAYO and Chemotherapy in Study 16113
Adverse Reactions | LIBTAYO and Chemotherapy (N=312) |  | Placebo and Chemotherapy (N=153)
Adverse Reactions | All Grades % | Grades 3 or 4 % | All Grades % | Grades 3 or 4 %
Skin and subcutaneous tissue disorders
Alopecia | 37 | 0 | 43 | 0
Rash [Rash is a composite term that includes rash, rash maculo-papular, dermatitis, psoriasis, rash papular, urticaria, dermatitis allergic, erythema, lichen planus, rash macular, rash pruritic, skin reaction, skin toxicity, skin exfoliation, and dermatitis acneiform] | 13 | 1.3 | 6 | 0
Musculoskeletal and connective tissue disorders
Musculoskeletal pain [Musculoskeletal pain is a composite term that includes arthralgia, back pain, pain in extremity, non-cardiac chest pain, myalgia, bone pain, musculoskeletal pain, neck pain, musculoskeletal chest pain, arthritis, and spinal pain] | 30 | 1.6 | 36 | 0
Gastrointestinal disorders
Nausea | 25 | 0 | 16 | 0
Constipation | 14 | 0.3 | 11 | 0
Vomiting | 12 | 0 | 10 | 0
Diarrhea | 11 | 1.3 | 7 | 0
General disorders and administration site conditions
Fatigue [Fatigue is a composite term that includes asthenia, fatigue, and malaise] | 23 | 3.8 | 18 | 2
Nervous system disorders
Peripheral neuropathy [Peripheral neuropathy is a composite term that includes peripheral sensory neuropathy, peripheral neuropathy, paresthesia, polyneuropathy, hypoesthesia, peripheral sensorimotor neuropathy, neuralgia, polyneuropathy in malignant disease, and toxic neuropathy] | 23 | 0 | 19 | 0
Metabolism and nutrition disorders
Decreased appetite | 17 | 1 | 12 | 0
Investigations
Weight decreased | 11 | 1.3 | 8 | 0
Respiratory, thoracic, and mediastinal disorders
Dyspnea [Dyspnea is a composite term that includes dyspnea and dyspnea exertional] | 13 | 2.2 | 7 | 0.7
Psychiatric disorders
Insomnia | 11 | 0 | 7 | 0
Toxicity was graded per National Cancer Institute Common Terminology Criteria for Adverse Events (NCI CTCAE) v. 4.03

Table 10: Grade 3 or 4 Laboratory Abnormalities Worsening from Baseline in ≥1% of Patients with Locally Advanced or Metastatic NSCLC Receiving LIBTAYO and Chemotherapy in Study 16113
Laboratory Abnormality | LIBTAYO and Chemotherapy | Placebo and Chemotherapy
Laboratory Abnormality | Grades 3 or 4 (%) [The denominator used to calculate the rate varied from 134 to 299 based on the number of patients with a baseline value and at least one post-treatment value.]
Chemistry
Hyperglycemia | 4 | 1.5
Increased alanine aminotransferase | 3 | 2.1
Increased creatinine | 2 | 1.4
Hypoalbuminemia | 1 | 0
Hematology
Anemia | 10 | 7
Neutrophil count decreased | 10 | 8
Lymphocyte count decreased | 7 | 8
White blood cell decreased | 6 | 4.1
Platelet count decreased | 4.7 | 0.7
Electrolytes
Hyponatremia | 6 | 4.1
Hypophosphatemia | 3.4 | 7
Hypocalcemia | 3 | 2.1
Hyperkalemia | 2.7 | 2.7
Hypermagnesemia | 2.4 | 2.8
Hypokalemia | 2.3 | 1.4
Hypercalcemia | 1.7 | 0.7
Hypernatremia | 1 | 0
Toxicity graded per NCI CTCAE v. 4.03

First-line treatment of NSCLC with LIBTAYO as a single agent

The safety of LIBTAYO was evaluated in 355 patients with locally advanced or metastatic NSCLC in Study 1624 [see Clinical Studies (14.3)]. Patients received LIBTAYO 350 mg every 3 weeks (n=355) or investigator's choice of chemotherapy (n=342), consisting of paclitaxel plus cisplatin or carboplatin; gemcitabine plus cisplatin or carboplatin; or pemetrexed plus cisplatin or carboplatin followed by optional pemetrexed maintenance. The median duration of exposure was 27.3 weeks (9 days to 115 weeks) in the LIBTAYO group and 17.7 weeks (18 days to 86.7 weeks) in the chemotherapy group. In the LIBTAYO group, 54% of patients were exposed to LIBTAYO for ≥6 months and 22% were exposed for ≥12 months.

The safety population characteristics were: median age of 63 years (31 to 79 years), 44% of patients 65 or older, 88% male, 86%White, 82% had metastatic disease and 18% had locally advanced disease, and ECOG performance score (PS) of 0 (27%) and 1 (73%).

LIBTAYO was permanently discontinued due to adverse reactions in 6% of patients; adverse reactions resulting in permanent discontinuation in at least 2 patients were pneumonitis, pneumonia, ischemic stroke, and increased aspartate aminotransferase. Serious adverse reactions occurred in 28% of patients. The most frequent serious adverse reactions in at least 2% of patients were pneumonia and pneumonitis.

Table 11 summarizes the adverse reactions that occurred in ≥10% of patients and Table 12 summarizes Grade 3 or 4 laboratory abnormalities in patients receiving LIBTAYO.

Table 11: Adverse Reactions in ≥10% of Patients with Locally Advanced or Metastatic NSCLC Receiving LIBTAYO in Study 1624
Adverse Reactions | LIBTAYO N=355 |  | Chemotherapy N=342
Adverse Reactions | All Grades % | Grades 3-4 % | All Grades % | Grades 3-4 %
Musculoskeletal and connective tissue disorders
Musculoskeletal pain [Musculoskeletal pain is a composite term that includes back pain, arthralgia, pain in extremity, musculoskeletal pain, musculoskeletal chest pain, bone pain, myalgia, neck pain, spinal pain, and musculoskeletal stiffness] | 26 | 0.6 | 27 | 1.5
Skin and subcutaneous tissue disorders
Rash [Rash is a composite term that includes rash, dermatitis, urticaria, rash maculo-papular, erythema, rash erythematous, rash pruritic, psoriasis, autoimmune dermatitis, dermatitis acneiform, dermatitis allergic, dermatitis atopic, dermatitis bullous, drug eruption, dyshidrotic eczema, lichen planus, and skin reaction] | 15 | 1.4 | 6 | 0
Blood and lymphatic system disorders
Anemia | 15 | 3.4 | 50 | 16
General disorders and administration site conditions
Fatigue [Fatigue is a composite term that includes fatigue, asthenia, and malaise] | 14 | 1.1 | 26 | 2
Metabolism and nutrition disorders
Decreased appetite | 12 | 0.6 | 18 | 0.3
Infections and infestations
Pneumonia [Pneumonia is a composite term that includes atypical pneumonia, embolic pneumonia, lower respiratory tract infection, lung abscess, paracancerous pneumonia, pneumonia, pneumonia bacterial, and pneumonia klebsiella] | 11 | 5 | 12 | 5
Respiratory, thoracic, and mediastinal disorders
Cough [Cough is a composite term that includes cough and productive cough] | 11 | 0 | 8 | 0.3
Toxicity was graded per National Cancer Institute Common Terminology Criteria for Adverse Events (NCI CTCAE) v.4.03

Table 12: Grade 3 or 4 Laboratory Abnormalities Worsening from Baseline in ≥1% of Patients with Locally Advanced or Metastatic NSCLC Receiving LIBTAYO in Study 1624
Laboratory Abnormality | LIBTAYO N=355 | Chemotherapy N=342
Laboratory Abnormality | Grades 3-4 [Percentages are based on the number of patients with at least 1 post-baseline value available for that parameter] %
Chemistry
Increased aspartate aminotransferase | 3.9 | 1.2
Increased alanine aminotransferase | 2.7 | 0.3
Increased alkaline phosphatase | 2.4 | 0.3
Increased blood bilirubin | 2.1 | 0.3
Hypoalbuminemia | 1.8 | 1.3
Increased creatinine | 1.2 | 1.6
Hematology
Lymphopenia | 7 | 9
Anemia | 2.7 | 16
Electrolytes
Hyponatremia | 6 | 7
Hyperkalemia | 4.2 | 1.9
Hypocalcemia | 3.9 | 3.4
Hypophosphatemia | 2.4 | 4.1
Hypermagnesemia | 2.1 | 1.6
Hypokalemia | 1.5 | 2.2
Hypercalcemia | 1.2 | 2.2
Toxicity graded per NCI CTCAE v. 4.03

8 USE IN SPECIFIC POPULATIONS

8.1 Pregnancy

Risk Summary

Based on its mechanism of action, LIBTAYO can cause fetal harm when administered to a pregnant woman [see Clinical Pharmacology (12.1)]. There are no available data on the use of LIBTAYO in pregnant women. Animal studies have demonstrated that inhibition of the PD-1/PD-L1 pathway can lead to increased risk of immune-mediated rejection of the developing fetus resulting in fetal death (see Data). Human IgG4 immunoglobulins (IgG4) are known to cross the placenta; therefore, LIBTAYO has the potential to be transmitted from the mother to the developing fetus. Advise women of the potential risk to a fetus.

In the U.S. general population, the estimated background risk of major birth defects and miscarriage in clinically recognized pregnancies is 2% to 4% and 15% to 20%, respectively.

Data

Animal Data

Animal reproduction studies have not been conducted with LIBTAYO to evaluate its effect on reproduction and fetal development. A central function of the PD-1/PD-L1 pathway is to preserve pregnancy by maintaining maternal immune tolerance to the fetus. In murine models of pregnancy, blockade of PD-L1 signaling has been shown to disrupt tolerance to the fetus and to result in an increase in fetal loss; therefore, potential risks of administering LIBTAYO during pregnancy include increased rates of abortion or stillbirth. As reported in the literature, there were no malformations related to the blockade of PD-1/PD-L1 signaling in the offspring of these animals; however, immune-mediated disorders occurred in PD-1 and PD-L1 knockout mice. Based on its mechanism of action, fetal exposure to cemiplimab-rwlc may increase the risk of developing immune-mediated disorders or altering the normal immune response.

8.2 Lactation

Risk Summary

There is no information regarding the presence of cemiplimab-rwlc in human milk, or its effects on the breastfed child or on milk production. Because of the potential for serious adverse reactions in breastfed children, advise women not to breastfeed during treatment and for at least 4 months after the last dose of LIBTAYO.

8.3 Females and Males of Reproductive Potential

Pregnancy Testing

Verify pregnancy status in females of reproductive potential prior to initiating LIBTAYO [see Use in Specific Populations (8.1)].

Contraception

LIBTAYO can cause fetal harm when administered to a pregnant woman [see Use in Specific Populations (8.1)].

Females

Advise females of reproductive potential to use effective contraception during treatment with LIBTAYO and for at least 4 months after the last dose.

8.4 Pediatric Use

The safety and effectiveness of LIBTAYO have not been established in pediatric patients.

The safety and efficacy of LIBTAYO as a single agent (Part 1, N=25) or in combination with radiation therapy (Part 2, N=22) were evaluated but not established in a two-part, open-label, multi-center trial (Study 1690, NCT03690869) in pediatric patients (birth to < 17 years) with relapsed or refractory solid tumors (Part 1) or relapsed or refractory CNS tumors (Parts 1 and 2) or newly diagnosed CNS tumors (Part 2). No new safety signals were observed in these pediatric patients.

Cemiplimab exposure in 46 pediatric patients aged 1 to < 17 years was within the range of values previously observed in adults given a similar dose based on body weight.

8.5 Geriatric Use

LIBTAYO as a Single Agent

Of the 1281 patients with advanced cancers who received LIBTAYO as a single agent in clinical studies, 26% were 65 years up to 75 years and 22% were 75 years or older. No overall differences in safety or effectiveness were observed between these patients and younger patients.

Of the 358 patients with mCSCC or laCSCC who received LIBTAYO as a single agent in Study 1540, 30% were 65 years up to 75 years and 48% were 75 years or older. No overall differences in safety or effectiveness were observed between these patients and younger patients.

Of the 205 adult patients with CSCC at high-risk of recurrence who received LIBTAYO as a single agent in the C-POST study, 39% were 65 years up to 75 years and 35% were 75 years or older. No overall differences in safety or effectiveness were observed between these patients and younger patients.

Of the 138 patients with BCC who received LIBTAYO as a single agent in Study 1620, 27% were 65 years up to 75 years, and 31% were 75 years or older. No overall differences in safety or effectiveness were observed between these patients and younger patients.

LIBTAYO in Combination with Platinum-based Chemotherapy

Of the 312 patients with NSCLC who received LIBTAYO in combination with platinum-based chemotherapy in Study 16113, 35% were 65 years up to 75 years and 6% were 75 years or older. No overall differences in safety or effectiveness were observed between these patients and younger patients.

11 DESCRIPTION

Cemiplimab-rwlc is a human programmed death receptor-1 (PD-1) blocking antibody. Cemiplimab-rwlc is a recombinant human IgG4 monoclonal antibody that binds to PD-1 and blocks its interaction with PD-L1 and PD-L2. Cemiplimab-rwlc is produced by recombinant DNA technology in Chinese hamster ovary (CHO) cell suspension culture. Cemiplimab-rwlc has an approximate molecular weight of 146 kDa.

LIBTAYO (cemiplimab-rwlc) injection for intravenous use is a sterile, preservative-free, clear to slightly opalescent, colorless to pale yellow solution with a pH of 6. The solution may contain trace amounts of translucent to white particles.

Each vial contains 350 mg of cemiplimab-rwlc. Each mL contains cemiplimab-rwlc 50 mg, L-histidine (0.74 mg), L-histidine monohydrochloride monohydrate (1.1 mg), sucrose (50 mg), L-proline (15 mg), polysorbate 80 (2 mg), and Water for Injection, USP.

12 CLINICAL PHARMACOLOGY

12.1 Mechanism of Action

Binding of the PD-1 ligands PD-L1 and PD-L2 to the PD-1 receptor found on T cells inhibits T-cell proliferation and cytokine production. Upregulation of PD-1 ligands occurs in some tumors and signaling through this pathway can contribute to inhibition of active T-cell immune surveillance of tumors.

Cemiplimab-rwlc is a recombinant human immunoglobulin G4 (IgG4) monoclonal antibody that binds to PD-1 and blocks its interaction with PD-L1 and PD-L2, releasing PD-1 pathway-mediated inhibition of the immune response, including the anti-tumor immune response. In syngeneic mouse tumor models, blocking PD-1 activity resulted in decreased tumor growth.

12.2 Pharmacodynamics

Cemiplimab exposure-response relationships and the time course of pharmacodynamic response are not fully characterized.

12.3 Pharmacokinetics

Cemiplimab-rwlc pharmacokinetics were observed at steady state in patients with various solid tumors and are presented as mean (% coefficient of variation) unless otherwise specified. The pharmacokinetics of cemiplimab-rwlc increase in a dose proportional manner over the dose range of 1 mg/kg to 10 mg/kg (0.2 to 2 times the highest recommended approved dose; assuming a 70 kg patient) administered intravenously every 2 weeks.

At a dosing regimen of 350 mg every 3 weeks, cemiplimab-rwlc minimum concentration is 59 mg/L (47%) and maximum concentration is 171 mg/L (27%). Steady-state is reached in about 4 months.

At a dosing regimen of 350 mg every 3 weeks for 12 weeks followed by 700 mg every 6 weeks, cemiplimab-rwlc minimum concentration after 30 weeks is 50 mg/L (32%).

Distribution

The volume of distribution of cemiplimab-rwlc is 5.9 L (29%).

Elimination

Cemiplimab-rwlc clearance after the first dose is 0.25 L/day (41%) and decreases over time by 11%, resulting in a steady-state clearance of 0.22 L/day (44%). The elimination half-life is 22 days (42%).

Specific Populations

No clinically significant differences in the pharmacokinetics of cemiplimab-rwlc were observed based on age (27 to 96 years), race [White (N=932), Asian (N=47), Black (N=21)], sex, body weight (31 to 172 kg), cancer type, albumin level (20 to 93 g/L), renal function (creatinine clearance determined by Cockcroft-Gault) and hepatic function (total bilirubin ≥1 to 3× ULN). The effect of severe hepatic impairment (total bilirubin 3× ULN) on the pharmacokinetics of cemiplimab-rwlc is unknown.

12.6 Immunogenicity

The observed incidence of anti-drug antibodies is highly dependent on the sensitivity and specificity of the assay. Differences in assay methods preclude meaningful comparisons of the incidence of anti-drug antibodies in the studies described below with the incidence of anti-drug antibodies in other studies, including those of cemiplimab-rwlc or of other cemiplimab products.

During a treatment period ranging from 8 to 19 months in 5 clinical studies, 2% (22/1029) of LIBTAYO-treated patients developed anti-cemiplimab-rwlc antibodies.

There was no clinically significant effect of anti-cemiplimab-rwlc antibodies on PK of cemiplimab-rwlc. Because of the low occurrence of anti-drug antibodies, the effect of these antibodies on the pharmacodynamics, safety, and/or effectiveness of cemiplimab products is unknown.

13 NONCLINICAL TOXICOLOGY

13.1 Carcinogenesis, Mutagenesis, Impairment of Fertility

No studies have been performed to assess the potential of cemiplimab-rwlc for carcinogenicity or genotoxicity.

In a 3-month repeat-dose toxicology study in sexually mature cynomolgus monkeys, there were no cemiplimab-rwlc-related effects on fertility parameters (menstrual cycle, semen analysis, or testicular measurements) or in male or female reproductive organs at doses up to the highest dose tested, 50 mg/kg/week (approximately 5.5 to 25.5 times the human exposure based on AUC at the clinical dose of 350 mg once every 3 weeks).

13.2 Animal Toxicology and/or Pharmacology

In animal models, inhibition of PD-L1/PD-1 signaling increased the severity of some infections and enhanced inflammatory responses. M. tuberculosis–infected PD-1 knockout mice exhibit markedly decreased survival compared with wild-type controls, which correlated with increased bacterial proliferation and inflammatory responses in these animals. PD-L1 and PD-1 knockout mice and mice receiving PD-L1 blocking antibody have also shown decreased survival following infection with lymphocytic choriomeningitis virus.

14 CLINICAL STUDIES

14.1 Cutaneous Squamous Cell Carcinoma (CSCC)

Advanced CSCC

The efficacy of LIBTAYO in patients with metastatic (nodal or distant) cutaneous squamous cell carcinoma (mCSCC) or locally advanced CSCC (laCSCC) who were not candidates for curative surgery or curative radiation was evaluated in two open-label, multi-center, non-randomized, multicohort studies: Study 1423 (NCT02383212) and Study 1540 (NCT02760498). Both studies excluded patients with autoimmune disease that required systemic therapy with immunosuppressant agents within 5 years; history of solid organ transplant; prior treatment with anti–PD-1/PD-L1 blocking antibodies or other immune checkpoint inhibitor therapy; infection with HIV, hepatitis B or hepatitis C; or ECOG PS ≥2.

Patients received LIBTAYO 3 mg/kg intravenously every 2 weeks for up to 48 weeks in Study 1423 or up to 96 weeks (Groups 1 and 2), or 350 mg every 3 weeks for up to 54 weeks (Group 3) in Study 1540. Treatment continued until progression of disease, unacceptable toxicity, or completion of planned treatment. Tumor response assessments were performed every 8 or 9 weeks. The major efficacy outcome measures were confirmed objective response rate (ORR), defined as complete response (CR) plus partial response (PR) as assessed by independent central review (ICR), and ICR-assessed duration of response (DOR). For patients with mCSCC without externally visible target lesions, ORR was determined by Response Evaluation Criteria in Solid Tumors (RECIST 1.1). For patients with externally visible target lesions (laCSCC and mCSCC), ORR was determined by a composite endpoint that integrated ICR assessments of radiologic data (RECIST 1.1) and digital medical photography (WHO criteria).

Study 1540

In the efficacy analysis of 193 patients with advanced CSCC enrolled in Study 1540 who received LIBTAYO at either 3 mg/kg every 2 weeks or 350 mg every three weeks, 115 had mCSCC and 78 had laCSCC. The median age was 72 years (38 to 96 years); 83% were male; 97% were White, 2% were Asian, 1% were Black or African American, and 1% were race unknown; 45% had ECOG PS 0 and 55% had ECOG PS 1; 34% received at least one prior anti-cancer systemic therapy; 81% received prior cancer-related surgery; and 68% received prior radiotherapy. Among patients with mCSCC, 77% had distant metastases and 23% had only nodal metastases.

For the responding patients presented in Table 13 below, the median time to response was 2.1 months (range: 1.7 to 22.8 months).

Efficacy results based on the final analysis of Study 1540 are presented in Table 13.

Table 13: Efficacy Results for Study 1540 in Advanced CSCC
Efficacy Endpoints [Median duration of follow up: mCSCC 3 mg/kg every 2 weeks: 18.5 months; laCSCC 3 mg/kg every 2 weeks: 15.5 months; mCSCC 350 mg every 3 weeks: 17.3 months; combined CSCC: 15.7 months] | Metastatic CSCC LIBTAYO 3 mg/kg every 2 weeks (Group 1) | Locally Advanced CSCC LIBTAYO 3 mg/kg every 2 weeks (Group 2) | Metastatic CSCC LIBTAYO 350 mg every 3 weeks (Group 3) | Combined CSCC
 | N = 59 | N = 78 | N = 56 | N = 193
Confirmed Objective Response Rate (ORR) (%)
ORR (95% CI) | 51 (37, 64) | 45 (34, 57) | 46 (33, 60) | 47 (40, 54)
Complete response rate [Only includes patients with complete healing of prior cutaneous involvement; laCSCC patients in Study 1540 required biopsy to confirm CR] | 20 | 13 | 20 | 17
Partial response rate | 31 | 32 | 27 | 30
Duration of Response (DOR)
Number of Responders | N = 30 | N = 35 | N = 26 | N = 91
Median DOR in months [Based on Kaplan-Meier estimate] (Range) | NR (2.8 – 38.9) | 42 (1.9 – 54.6) | 41 (4.2 – 46.3) | 41 (1.9 – 54.6)
Patients with observed DOR ≥6 months, n (%) [The numerator includes the number of patients whose observed DOR reached at least the specified times of 6 or 12 months. Patients who did not have the opportunity to reach the specified timepoint were included in the denominator only] | 28 (93%) | 31 (89%) | 25 (96%) | 84 (92%)
Patients with observed DOR ≥12 months, n (%) | 23 (77%) | 24 (69%) | 23 (88%) | 70 (77%)
CI: confidence interval; NR: not reached

Study 1423

Among 26 CSCC patients in Study 1423, 16 had mCSCC and 10 had laCSCC. The median age was 73 years (52 to 88 years); 81% of patients were male; 92% of patients were White; the ECOG PS was 0 (38%) and 1 (62%); 58% of patients had received at least 1 prior anti-cancer systemic therapy; 92% of patients had received prior cancer-related surgery and 81% had received prior radiotherapy. One patient in the mCSCC group was dosed at 1 mg/kg. The rest received 3 mg/kg every 2 weeks.

With a median duration of follow-up of 13.3 months, the confirmed ORR was 50% (95% CI: 30, 70); all responses were PRs. The median time to response was 1.9 months (range: 1.7 to 7.3 months) and 85% of responders had a DOR ≥6 months.

Adjuvant treatment of CSCC at high risk of recurrence after surgery and radiation.

The efficacy of LIBTAYO was evaluated in the C-POST study (NCT03969004), a randomized, double-blind, multicenter, placebo-controlled trial in 415 patients with CSCC at high risk of recurrence after surgery and radiation. Patients were required to complete adjuvant radiation therapy within 2 to 10 weeks of randomization. High risk of recurrence was defined as at least one of the following features:

- Nodal Features:
  - Extracapsular extension (ECE) with ≥1 node ≥20 mm, or
  - ≥3 involved lymph nodes regardless of ECE
- Non-Nodal Features:
  - In-transit metastases (skin or subcutaneous metastases > 2 cm from the primary lesion but not beyond the regional nodal basin),
  - Invasion of the skeleton or base of the skull (T4 Lesion),
  - Perineural Invasion, or
  - Locally recurrent tumor with ≥1 additional adverse feature listed below:
    - Multiple ipsilateral nodes
    - ≥T3 (≥4 cm diameter or bone erosion or invasion >6 mm)
    - Poorly differentiated histology and recurrent lesion ≥20 mm diameter

The study excluded patients with autoimmune disease that required systemic therapy with immunosuppressant agents within 5 years; history of solid organ transplant; prior allogeneic or autologous stem cell transplantation; uncontrolled HIV, hepatitis B or hepatitis C infection, or ECOG PS ≥2.

Patients were randomized 1:1 to receive LIBTAYO (N=209) or placebo (n=206). In the LIBTAYO arm, 171 patients received 350 mg LIBTAYO intravenously every 3 weeks for 12 weeks, followed by 700 mg LIBTAYO intravenously every 6 weeks for an additional 36 weeks, and 38 patients received 350 mg LIBTAYO intravenously every 3 weeks for up to 48 weeks. Treatment continued until disease recurrence, unacceptable toxicity, or up to 48 weeks.

The major efficacy outcome measure was disease-free survival (DFS) defined as time from randomization to the first documented disease recurrence by investigator assessment or death due to any cause. Overall survival was an additional outcome measure.

The median age was 71 years (range: 33 to 95); 84% were male; 91% were White, 3.1% were Asian, 5.4% were unknown or not reported, 0.5% were other; 9.4% were Hispanic or Latino, 83.4% were not Hispanic or Latino, 7% were unknown or not reported; 64% had ECOG PS of 0 and 36% had ECOG PS of 1. The location of tumor was head and neck (HN) in 83% of patients and non-HN in 17% of patients. The high-risk of recurrence feature was nodal in 58% of patients and non-nodal in 42% of patients.

A statistically significant improvement in DFS was demonstrated in patients randomized to LIBTAYO compared with placebo. Improvement in DFS was similar in both dosage regimens. Efficacy results in C-POST study are summarized in Table 14 and Figure 1.

Table 14: Efficacy Results for the C-POST Study in Patients with CSCC at High Risk of Recurrence in the Adjuvant Setting
Efficacy Endpoints | LIBTAYO | Placebo
Efficacy Endpoints | N = 209 | N = 206
Disease-Free Survival (DFS)
Number of events, n (%) | 24 (12%) | 65 (32%)
Disease recurrences, n (%); - Distant recurrence, n (%) - Locoregional recurrence, n (%) | 18 (9%) 10 (4.8%) 8 (3.8%) | 61 (30%) 26 (13%) 35 (17%)
Deaths, n (%) | 6 (2.9%) | 4 (1.9%)
Median (95% CI) in months [Based on Kaplan-Meier method] | NR (NE, NE) | 49.4 (48.5, NE)
Hazard ratio (95% CI) [Based on stratified proportional hazards model] | 0.32 (0.20, 0.51)
p-value [Based on a two-sided stratified log-rank test] | <0.0001
CI: confidence interval; NE: not evaluable; NR: not reached

Figure 1: Kaplan-Meier Curve of DFS in the C-POST study

14.2 Basal Cell Carcinoma (BCC)

The efficacy of LIBTAYO in 138 patients with advanced basal cell carcinoma (BCC) [unresectable locally advanced (laBCC) or metastatic (nodal or distant) (mBCC)] who had progressed on hedgehog pathway inhibitor (HHI) therapy, had not had an objective response after 9 months on HHI therapy, or were intolerant of prior HHI therapy was evaluated in Study 1620 (NCT03132636), an open-label, multi-center, non-randomized study. The study excluded patients with autoimmune disease that required systemic therapy with immunosuppressant agents within 5 years; history of solid organ transplant; prior treatment with anti–PD-1/PD-L1 therapy or other immune checkpoint inhibitor therapy; infection with HIV, hepatitis B or hepatitis C; or ECOG performance score (PS) ≥2.

Patients received LIBTAYO 350 mg every 3 weeks for up to 93 weeks until disease progression, unacceptable toxicity, or completion of planned treatment. Tumor assessments were performed every 9 weeks for the first 45 weeks of treatment and every 12 weeks thereafter. The major efficacy outcome measures were confirmed objective response rate (ORR) and duration of response (DOR) as assessed by independent central review (ICR). For patients with mBCC without externally visible target lesions, ORR was determined by Response Evaluation Criteria in Solid Tumors (RECIST 1.1). For patients with externally visible target lesions (laBCC and mBCC), ORR was determined by a composite endpoint that integrated ICR assessments of radiologic data (RECIST 1.1) and digital medical photography (WHO criteria).

A total of 138 patients with advanced BCC were included in the efficacy analysis of Study 1620. Of these, 39% had mBCC and 61% had laBCC. In patients with laBCC, the median age was 70 years (42 to 89 years); 67% were male; 68% were White and 32% were race not reported/unknown; 61% had ECOG PS 0 and 39% had ECOG PS 1; 83% had received at least 1 prior cancer-related surgery; and 50% had received prior radiotherapy. In patients with mBCC, the median age was 63.5 years (38 to 90 years); 70% were male; 87% were White and 13% were race not reported/unknown; 67% had ECOG PS 0 and 33% had ECOG PS 1; 85% had received at least 1 prior cancer-related surgery; and 59% had received prior radiotherapy. Among patients with mBCC, 35% had distant metastases only, 9% had nodal disease only, and 54% had both distant and nodal disease.

Efficacy results are presented in Table 15. For the responding patients, the median time to response was 3.1 months (range 2 to 10.5 months) for the mBCC group and 4.3 months (range 2.1 to 21.4 months) for the laBCC group.

Table 15: Efficacy Results for Study 1620 in BCC
Efficacy Endpoints [Median duration of follow up: mBCC 8.4 months; laBCC 15.9 months] | Metastatic BCC | Locally Advanced BCC
 | N = 54 | N = 84
Confirmed Objective Response Rate (ORR) (%)
ORR (95% CI) | 22 (12, 36) | 32 (22, 43)
Complete response rate | 1.9 | 7
Partial response rate | 20 | 25
Duration of Response
Number of Responders | N = 12 | N = 27
Median DOR in months [Based on Kaplan-Meier estimate] (Range) | 16.7 (9.0 – 25.8+) | NR (2.1 – 36.8+)
Patients with observed DOR ≥6 months, n (%) | 12 (100%) | 23 (85%)
CI: confidence interval; NR: not reached; +: denotes ongoing at last assessment

14.3 Non-Small Cell Lung Cancer (NSCLC)

First-line treatment of NSCLC with LIBTAYO in combination with platinum-based chemotherapy

The efficacy of LIBTAYO in combination with platinum-based chemotherapy was evaluated in Study 16113 (NCT03409614), a randomized, multi-center, double-blind, active-controlled trial in 466 patients with locally advanced NSCLC who were not candidates for surgical resection or definitive chemoradiation or with metastatic NSCLC who had not previously received systemic treatment for metastatic NSCLC. Patients were eligible regardless of tumor PD-L1 expression status.

Patients with EGFR, ALK or ROS1 genomic tumor aberrations; a medical condition that required systemic immunosuppression; or ongoing or recent autoimmune disease that required systemic therapy were ineligible. Patients with a history of brain metastases were eligible if they had been adequately treated and had neurologically returned to baseline for at least 2 weeks prior to randomization.

Randomization was stratified by histology (non-squamous vs squamous) and PD-L1 expression (<1% versus 1% to 49% versus ≥50%) according to the VENTANA PD-L1 (SP263) assay. Patients were randomized (2:1) to receive either:

- LIBTAYO 350 mg intravenously (IV) every 3 weeks for 108 weeks plus platinum-based chemotherapy every 3 weeks for 4 cycles, or
- placebo IV every 3 weeks for 108 weeks plus platinum-based chemotherapy every 3 weeks for 4 cycles.

Platinum-based chemotherapy in either arm consisted of carboplatin AUC of 5 or 6 and paclitaxel 200 mg/m^2; cisplatin 75 mg/m^2 and paclitaxel 200 mg/m^2; carboplatin AUC of 5 or 6 and pemetrexed 500 mg/m^2; or cisplatin 75 mg/m^2 and pemetrexed 500 mg/m^2. Maintenance pemetrexed was mandatory for patients with non-squamous NSCLC who received a pemetrexed-containing chemotherapy regimen in the first 4 treatment cycles.

Study treatment continued until RECIST 1.1-defined progressive disease, unacceptable toxicity, or 108 weeks. Assessment of tumor status was performed every 9 weeks during year 1 and every 12 weeks after year 1. The major efficacy outcome measure was overall survival (OS). Additional efficacy outcome measures were progression-free survival (PFS) and overall response rate (ORR) as assessed by blinded independent central review (BICR).

The study population characteristics were: median age of 63 years (range: 25 to 84), 40% age 65 or older; 84% male; 87% White, 13% Asian. Fifteen percent had Eastern Cooperative Oncology Group (ECOG) Performance Status (PS) 0 and 84% had ECOG PS 1; 85% had metastatic disease and 15% had stage IIIB or IIIC disease and were not candidates for surgical resection or definitive chemoradiation per investigator assessment; 57% had non-squamous and 43% had squamous histology; and 7% had history of treated brain metastases at baseline.

The trial demonstrated a statistically significant improvement in OS for patients randomized to LIBTAYO in combination with chemotherapy compared with placebo in combination with chemotherapy.

Efficacy results are presented in Table 16 and Figure 2.

Table 16: Efficacy Results from Study 16113 in Non-Small Cell Lung Cancer
Endpoints | LIBTAYO and Chemotherapy N=312 | Placebo and Chemotherapy N=154
Overall Survival
Deaths, n (%) | 132 (42) | 82 (53)
Median in months (95% CI) [Based on Kaplan-Meier method] | 21.9 (15.5, NE) | 13.0 (11.9, 16.1)
Hazard ratio (95% CI) [Based on stratified proportional hazards model] | 0.71 (0.53, 0.93)
p-value [Based on a two-sided p-value] | 0.0140
Progression-free Survival per BICR
Events, n (%) | 204 (65) | 122 (79)
Median in months (95% CI) | 8.2 (6.4, 9.3) | 5.0 (4.3, 6.2)
Hazard ratio (95% CI) | 0.56 (0.44, 0.70)
p-value | <0.0001
Overall Response Rate per BICR (%)
ORR (95% CI) [Clopper-Pearson exact confidence interval] | 43 (38, 49) | 23 (16, 30)
Complete response (CR) rate | 2.6 | 0
Partial response (PR) rate | 41 | 23
p-value | <0.0001
Duration of Response per BICR
Median in months (range) | 15.6 (1.7, 18.7+) | 7.3 (1.8, 18.8+)
BICR: blinded independent central review; CI: confidence interval; NE: not evaluable; +: ongoing response

Figure 2: Kaplan-Meier Curve for OS from Study 16113

First-line treatment of NSCLC with LIBTAYO as a single agent

The efficacy of LIBTAYO was evaluated in Study 1624 (NCT03088540), a randomized, multi-center, open-label, active-controlled trial in 710 patients with locally advanced NSCLC who were not candidates for surgical resection or definitive chemoradiation, or with metastatic NSCLC.

Only patients whose tumors had high PD-L1 expression [Tumor Proportion Score (TPS) ≥50%] as determined by an immunohistochemistry assay using the PD-L1 IHC 22C3 pharmDx kit and who had not received prior systemic treatment for metastatic NSCLC were eligible.

Patients with EGFR, ALK or ROS1 genomic tumor aberrations; a medical condition that required systemic immunosuppression; autoimmune disease that required systemic therapy within 2 years of treatment; or who had never smoked were ineligible. Patients with a history of brain metastases were eligible if they had been adequately treated and had neurologically returned to baseline for at least 2 weeks prior to randomization.

Randomization was stratified by histology (non-squamous vs squamous) and geographic region (Europe vs Asia vs Rest of world). Patients were randomized (1:1) to receive LIBTAYO 350 mg intravenously (IV) every 3 weeks for up to 108 weeks or a platinum-doublet chemotherapy regimen for 4 to 6 cycles followed by optional pemetrexed maintenance for patients with non-squamous histology who received a pemetrexed containing regimen.

Treatment with LIBTAYO continued until RECIST 1.1-defined progressive disease, unacceptable toxicity, or up to 108 weeks. Patients who experienced IRC-assessed RECIST 1.1-defined progressive disease on LIBTAYO therapy were permitted to continue treatment with LIBTAYO (up to an additional 108 weeks) with the addition of 4 cycles of histology-specific chemotherapy until further progression was observed. Of the 203 patients randomized to receive chemotherapy who had IRC-assessed RECIST 1.1- defined disease progression, 150 (74%) patients crossed over to treatment with LIBTAYO. Assessment of tumor status was performed every 9 weeks. The major efficacy outcome measures were overall survival (OS) and progression-free survival (PFS). An additional efficacy outcome measure was overall response rate (ORR).

The study population characteristics were: median age of 63 years (range: 31 to 84), 45% age 65 or older; 85% male; 86% White, 11% Asian, and 0.6% Black. Nine percent were Hispanic or Latino. Twenty-seven percent had ECOG PS 0 and 73% had ECOG PS 1; 84% had metastatic disease and 16% had stage IIIB or IIIC disease and were not candidates for surgical resection or definitive chemoradiation per investigator assessment; 56% had non-squamous and 44% had squamous histology; and 12% had history of treated brain metastases at baseline.

The trial demonstrated a statistically significant improvement in OS and PFS for patients randomized to LIBTAYO as compared with chemotherapy.

Efficacy results are presented in Table 17 and Figure 3.

Table 17: Efficacy Results from Study 1624 in Non-Small Cell Lung Cancer
Endpoints | LIBTAYO N=356 | Chemotherapy N=354
Overall Survival
Number of deaths (%) | 108 (30) | 141 (40)
Median in months (95% CI) [Based on Kaplan-Meier method] | 22.1 (17.7, NE) | 14.3 (11.7, 19.2)
Hazard ratio (95% CI) [Based on stratified proportional hazards model] | 0.68 (0.53, 0.87)
p-value | 0.0022
Progression-free Survival per BICR
Number of events (%) | 201 (57) | 262 (74)
Median in months (95% CI) | 6.2 (4.5, 8.3) | 5.6 (4.5, 6.1)
Hazard ratio (95% CI) | 0.59 (0.49, 0.72)
p-value | <0.0001
Overall Response Rate per BICR (%) [Clopper-Pearson exact confidence interval]
ORR (95% CI) | 37 (32, 42) | 21 (17, 25)
Complete response (CR) rate | 3 | 1
Partial response (PR) rate | 33 | 20
Duration of Response per BICR
Median in months (range) | 21.0 (1.9+, 23.3+) | 6.0 (1.3+, 16.5+)
BICR: blinded independent central review; CI: confidence interval; NE: not evaluable; +: ongoing response

Figure 3: Kaplan-Meier Curve for OS from Study 1624

16 HOW SUPPLIED/STORAGE AND HANDLING

LIBTAYO (cemiplimab-rwlc) injection is a clear to slightly opalescent, colorless to pale yellow solution that may contain trace amounts of translucent to white particles. It is supplied in a carton containing 1 single-dose vial of:

- 350 mg/7 mL (50 mg/mL) (NDC 61755-008-01)

STORAGE AND HANDLING

Store in a refrigerator at 2°C to 8°C (36°F to 46°F) in the original carton. Protect from light.

Do not freeze or shake.

17 PATIENT COUNSELING INFORMATION

Advise the patient to read the FDA-approved patient labeling (Medication Guide).

Immune-Mediated Adverse Reactions

Advise patients that LIBTAYO can cause immune-mediated adverse reactions including the following [see Warnings and Precautions (5.1)]:

- Pneumonitis: Advise patients to contact their healthcare provider immediately for signs or symptoms of pneumonitis, including new or worsening symptoms of cough, chest pain, or shortness of breath.
- Colitis: Advise patients to contact their healthcare provider immediately for signs or symptoms of colitis, including diarrhea, blood or mucus in stools, or severe abdominal pain.
- Hepatitis: Advise patients to contact their healthcare provider immediately for signs or symptoms of hepatitis.
- Endocrinopathies: Advise patients to contact their healthcare provider immediately for signs or symptoms of hypothyroidism, hyperthyroidism, adrenal insufficiency, hypophysitis, or type 1 diabetes mellitus.
- Nephritis: Advise patients to contact their healthcare provider immediately for signs or symptoms of nephritis.
- Dermatologic Adverse Reactions: Advise patients to contact their healthcare provider immediately if they develop a new rash.
- Other Immune-Mediated Adverse Reactions:
  - Advise patients that immune-mediated adverse reactions can occur and may involve any organ system, and to contact their healthcare provider immediately for any new or worsening signs or symptoms [see Warnings and Precautions (5.1)].
  - Advise patients of the risk of solid organ transplant rejection and other transplant (including corneal graft) rejection and to contact their healthcare provider immediately for signs or symptoms of organ transplant rejection [see Warnings and Precautions (5.1)].

Infusion-Related Reactions

Advise patients to contact their healthcare provider immediately for signs or symptoms of infusion-related reactions [see Warnings and Precautions (5.2)].

Complications of Allogeneic HSCT

Advise patients to contact their healthcare provider immediately if they develop signs or symptoms of post-allogeneic HSCT complications [see Warnings and Precautions (5.3)].

Embryo-Fetal Toxicity

Advise females of reproductive potential that LIBTAYO can cause harm to a fetus and to inform their healthcare provider of a known or suspected pregnancy [see Warnings and Precautions (5.4) and Use in Specific Populations (8.1, 8.3)].

Advise females of reproductive potential to use effective contraception during treatment and for at least 4 months after the last dose of LIBTAYO [see Use in Specific Populations (8.3)].

Lactation

Advise female patients not to breastfeed while taking LIBTAYO and for at least 4 months after the last dose [see Use in Specific Populations (8.2)].

Manufactured by:

Regeneron Pharmaceuticals, Inc.
777 Old Saw Mill River Road
Tarrytown, NY 10591-6707
U.S. License No. 1760

Marketed by:
Regeneron Pharmaceuticals, Inc. (Tarrytown, NY 10591)
©2025 Regeneron Pharmaceuticals, Inc.

All rights reserved.

MEDICATION GUIDE
LIBTAYO® (Lib-TIE-oh)
(cemiplimab-rwlc)
injection

What is the most important information I should know about LIBTAYO?
LIBTAYO is a medicine that may treat certain types of cancers by working with your immune system. LIBTAYO can cause your immune system to attack normal organs and tissues in any area of your body and can affect the way they work. These problems can sometimes become severe or life threatening and can lead to death. You can have more than one of these problems at the same time. These problems may happen anytime during treatment or even after your treatment has ended.
Call or see your healthcare provider right away if you develop any new or worsening signs or symptoms, including:
Lung problems.

- cough

- shortness of breath

- chest pain

Intestinal problems.

- diarrhea (loose stools) or more frequent bowel movements than usual
- stools that are black, tarry, sticky, or have blood or mucus
- severe stomach-area (abdomen) pain or tenderness

Liver problems.

- yellowing of your skin or the whites of your eyes
- severe nausea or vomiting
- pain on the right side of your stomach-area (abdomen)

- dark urine (tea colored)
- bleeding or bruising more easily than normal

Hormone gland problems.

- headache that will not go away or unusual headaches
- eye sensitivity to light
- eye problems
- rapid heartbeat
- increased sweating
- extreme tiredness
- weight gain or weight loss
- feeling more hungry or thirsty than usual

- urinating more often than usual
- hair loss
- feeling cold
- constipation
- your voice gets deeper
- dizziness or fainting
- changes in mood or behavior, such as decreased sex drive, irritability, or forgetfulness

Kidney problems.

- decrease in your amount of urine
- blood in your urine

- swelling of your ankles
- loss of appetite

Skin problems.

- rash
- itching
- skin blistering or peeling

- painful sores or ulcers in mouth or nose, throat, or genital area
- fever or flu-like symptoms
- swollen lymph nodes

Problems can also happen in other organs and tissues. These are not all of the signs and symptoms of immune system problems that can happen with LIBTAYO. Call or see your healthcare provider right away for any new or worsening signs or symptoms which may include:

- chest pain, irregular heartbeat, shortness of breath or swelling of ankles
- confusion, sleepiness, memory problems, changes in mood or behavior, stiff neck, balance problems, tingling or numbness of the arms or legs
- double vision, blurry vision, sensitivity to light, eye pain, changes in eyesight
- persistent or severe muscle pain or weakness, muscle cramps
- low red blood cells, bruising

Infusion reactions that can sometimes be severe or life-threatening. Signs and symptoms of infusion reactions may include:

- nausea
- vomiting
- chills or shaking
- itching or rash
- flushing
- shortness of breath or wheezing

- dizziness
- feel like passing out
- fever
- back or neck pain
- facial swelling

Rejection of a transplanted organ or tissue. Your healthcare provider should tell you what signs and symptoms you should report and monitor you, depending on the type of organ or tissue transplant that you have had.
Complications, including graft-versus-host disease (GVHD), in people who have received a bone marrow (stem cell) transplant that uses donor stem cells (allogeneic). These complications can be serious and can lead to death. These complications may happen if you underwent transplantation either before or after being treated with LIBTAYO. Your healthcare provider will monitor you for these complications.
Getting medical treatment right away may help keep these problems from becoming more serious. Your healthcare provider will check you for these problems during your treatment with LIBTAYO. Your healthcare provider may treat you with corticosteroid or hormone replacement medicines. Your healthcare provider may also need to delay or completely stop treatment with LIBTAYO if you have severe side effects.

What is LIBTAYO?
LIBTAYO is a prescription medicine used to treat adults with:

- a type of skin cancer called cutaneous squamous cell carcinoma (CSCC).
  - LIBTAYO may be used:
    - to treat CSCC that has spread or cannot be cured by surgery or radiation, or
    - to help prevent CSCC from coming back if your CSCC is at high risk of coming back after it has been removed by surgery and radiation.
- a type of skin cancer called basal cell carcinoma (BCC).
  - LIBTAYO may be used when your BCC cannot be removed by surgery (locally advanced BCC) or when it has spread (metastatic BCC), and
    - you have previously received treatment with a hedgehog pathway inhibitor (HHI), or
    - you cannot receive treatment with a HHI.
- a type of lung cancer called non-small cell lung cancer (NSCLC).
  - LIBTAYO may be used in combination with chemotherapy that contains a platinum medicine as your first treatment when your lung cancer:
    - has not spread outside your chest (locally advanced lung cancer) and you cannot have surgery or chemotherapy with radiation, or
    - your lung cancer has spread to other areas of your body (metastatic lung cancer), and
    - your tumor does not have an abnormal "EGFR", "ALK" or "ROS1" gene.
  - LIBTAYO may be used alone as your first treatment when your lung cancer:
    - has not spread outside your chest (locally advanced lung cancer) and you cannot have surgery or chemotherapy with radiation, or
    - your lung cancer has spread to other areas of your body (metastatic lung cancer), and
    - your tumor tests positive for high "PD-L1" and
    - your tumor does not have an abnormal "EGFR", "ALK" or "ROS1" gene

It is not known if LIBTAYO is safe and effective in children.

Before you receive LIBTAYO, tell your healthcare provider about all your medical conditions, including if you:

- have immune system problems such as Crohn's disease, ulcerative colitis, or lupus
- have received an organ or tissue transplant, including corneal transplant
- have received or plan to receive a stem cell transplant that uses donor stem cells (allogeneic)
- have received radiation treatment to your chest area
- have a condition that affects your nervous system, such as myasthenia gravis or Guillain-Barré syndrome
- are pregnant or plan to become pregnant. LIBTAYO can harm your unborn baby.
  Females who are able to become pregnant:
  - Your healthcare provider will give you a pregnancy test before you start treatment with LIBTAYO.
  - You should use an effective method of birth control during your treatment and for at least 4 months after the last dose of LIBTAYO. Talk to your healthcare provider about birth control methods that you can use during this time.
  - Tell your healthcare provider right away if you become pregnant or think you may be pregnant during treatment with LIBTAYO.
- are breastfeeding or plan to breastfeed. It is not known if LIBTAYO passes into your breast milk. Do not breastfeed during treatment and for at least 4 months after the last dose of LIBTAYO.

Tell your healthcare provider about all the medicines you take, including prescription and over-the-counter medicines, vitamins, and herbal supplements.

How will I receive LIBTAYO?

- Your healthcare provider will give you LIBTAYO into your vein through an intravenous (IV) line over 30 minutes.
- LIBTAYO is usually given every 3 weeks or every 6 weeks depending on the dose of LIBTAYO you are receiving.
- Your healthcare provider will decide how many treatments you will need.
- Your healthcare provider will do blood tests to check you for side effects.

If you miss any appointments, call your healthcare provider as soon as possible to reschedule your appointment.

What are the possible side effects of LIBTAYO?
LIBTAYO can cause serious side effects.

- See "What is the most important information I should know about LIBTAYO?"

The most common side effects of LIBTAYO when used alone to treat CSCC that has spread or cannot be cured by surgery or radiation, BCC or NSCLC include:

- tiredness
- muscle or bone pain
- rash

- diarrhea
- low levels of red blood cells (anemia)

The most common side effects of LIBTAYO when used alone to help prevent CSCC from coming back include:

- rash
- itching

The most common side effects of LIBTAYO when used in combination with platinum-containing chemotherapy to treat NSCLC include:

- hair loss
- muscle or bone pain
- nausea

- tiredness
- numbness, pain, tingling or burning in your hands or feet
- decreased appetite

These are not all the possible side effects of LIBTAYO.
Call your doctor for medical advice about side effects. You may report side effects to FDA at 1-800-FDA-1088.

General information about the safe and effective use of LIBTAYO.
Medicines are sometimes prescribed for purposes other than those listed in a Medication Guide. You can ask your pharmacist or healthcare provider for information about LIBTAYO that is written for health professionals.

What are the ingredients of LIBTAYO?
Active ingredient: cemiplimab-rwlc
Inactive ingredients: L-histidine, L-histidine monohydrochloride monohydrate, sucrose, L-proline, Polysorbate 80, and Water for Injection.
Manufactured by: Regeneron Pharmaceuticals, Inc. 777 Old Saw Mill River Road Tarrytown, NY 10591-6707 U.S. License No. 1760
Marketed by: Regeneron Pharmaceuticals, Inc. (Tarrytown, NY 10591)
For more information, call 1-877-542-8296
©2025 Regeneron Pharmaceuticals, Inc.
All rights reserved.

This Medication Guide has been approved by the U.S. Food and Drug Administration.

Revised: October 2025

PRINCIPAL DISPLAY PANEL - 350 mg/7 mL Vial Carton

NDC 61755-008-01
Rx only

LIBTAYO®
(cemiplimab-rwlc)
Injection

350 mg/7 mL (50 mg/mL)

For Intravenous Infusion After Dilution
Single-Dose Vial

Discard unused portion.

Do not use vial if seal is broken or missing.
Dispense the enclosed Medication Guide to each patient.

REGENERON